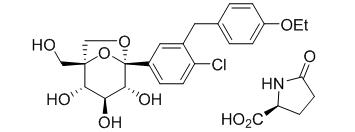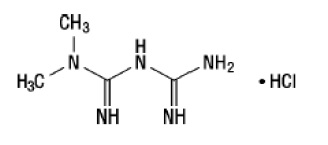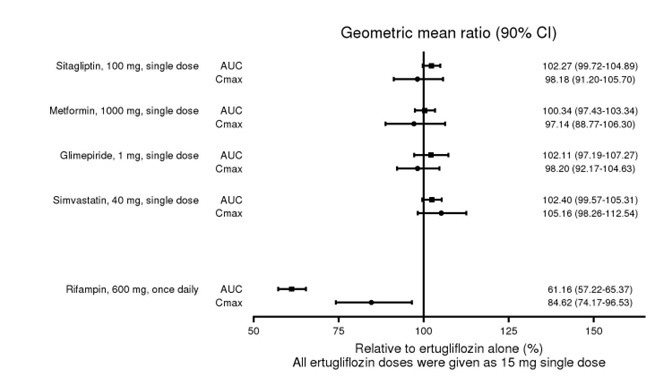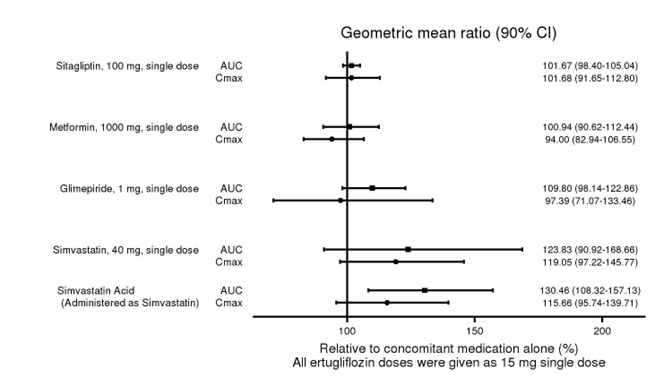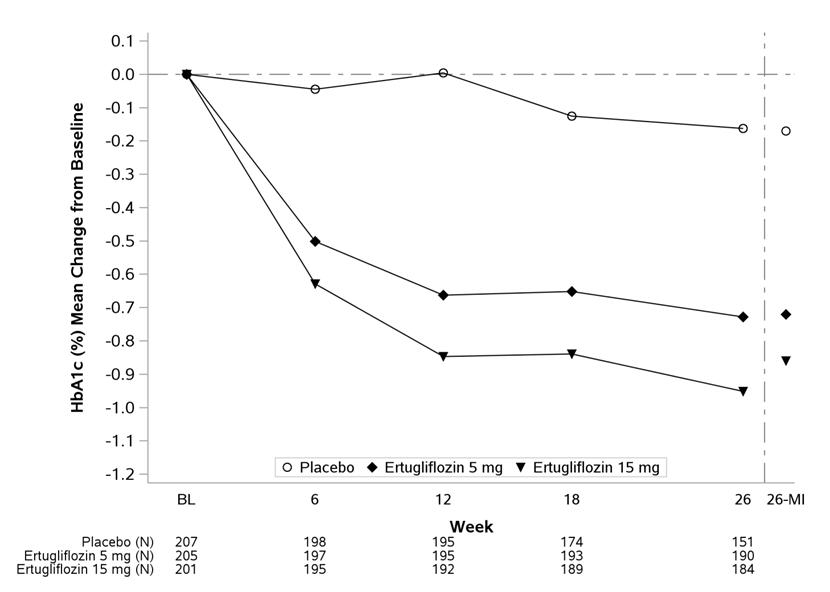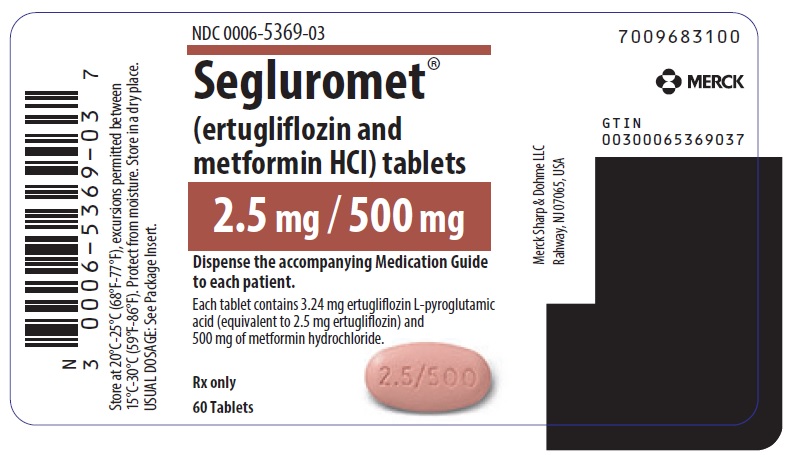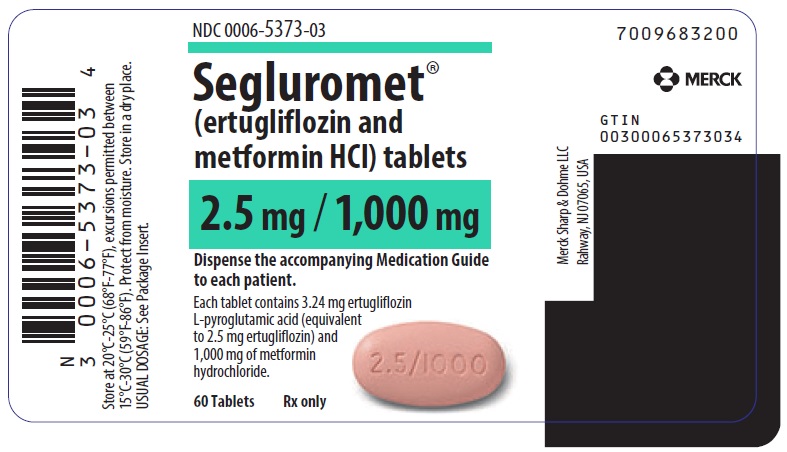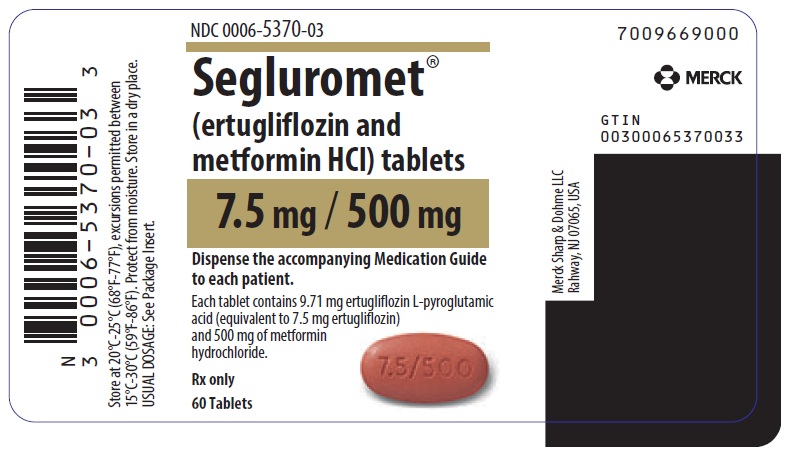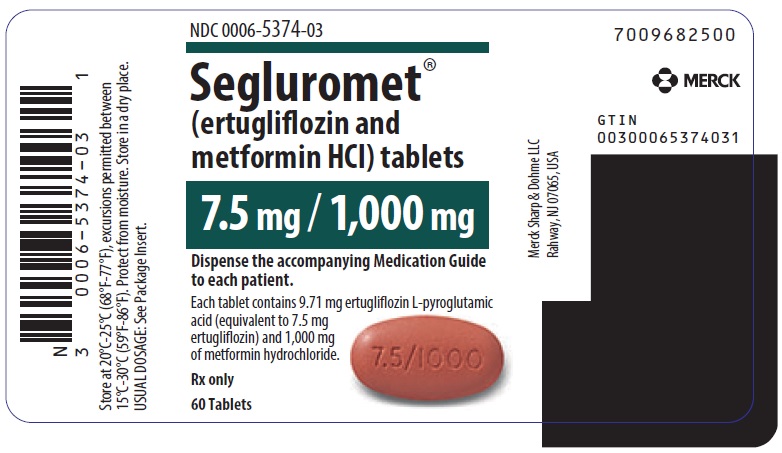 DRUG LABEL: SEGLUROMET
NDC: 0006-5369 | Form: TABLET, FILM COATED
Manufacturer: Merck Sharp & Dohme LLC
Category: prescription | Type: HUMAN PRESCRIPTION DRUG LABEL
Date: 20241220

ACTIVE INGREDIENTS: ERTUGLIFLOZIN PIDOLATE 2.5 mg/1 1; METFORMIN HYDROCHLORIDE 500 mg/1 1
INACTIVE INGREDIENTS: POVIDONE, UNSPECIFIED; MICROCRYSTALLINE CELLULOSE; CROSPOVIDONE; SODIUM LAURYL SULFATE; MAGNESIUM STEARATE; HYPROMELLOSE, UNSPECIFIED; HYDROXYPROPYL CELLULOSE, UNSPECIFIED; TITANIUM DIOXIDE; FERRIC OXIDE RED; CARNAUBA WAX

HIGHLIGHTS OF PRESCRIBING INFORMATION

These highlights do not include all the information needed to use SEGLUROMET safely and effectively. See full prescribing information for SEGLUROMET.
SEGLUROMET® (ertugliflozin and metformin hydrochloride) tablets, for oral use
Initial U.S. Approval: 2017

RECENT MAJOR CHANGES

Dosage and Administration (2.4) | 12/2024
Warnings and Precautions (5.3, 5.6) | 12/2024

WARNING: LACTIC ACIDOSIS

See full prescribing information for complete boxed warning.

- Postmarketing cases of metformin-associated lactic acidosis have resulted in death, hypothermia, hypotension, and resistant bradyarrhythmias. Symptoms included malaise, myalgias, respiratory distress, somnolence, and abdominal pain. Laboratory abnormalities included elevated blood lactate levels, anion gap acidosis, increased lactate/pyruvate ratio, and metformin plasma levels generally >5 mcg/mL. (5.1)
- Risk factors include renal impairment, concomitant use of certain drugs, age ≥65 years old, radiological studies with contrast, surgery and other procedures, hypoxic states, excessive alcohol intake, and hepatic impairment. Steps to reduce the risk of and manage metformin-associated lactic acidosis in these high risk groups are provided in the Full Prescribing Information. (5.1)
- If lactic acidosis is suspected, discontinue SEGLUROMET and institute general supportive measures in a hospital setting. Prompt hemodialysis is recommended. (5.1)

1 INDICATIONS AND USAGE

SEGLUROMET is a combination of ertugliflozin, a sodium glucose co-transporter 2 (SGLT2) inhibitor, and metformin, a biguanide, indicated as an adjunct to diet and exercise to improve glycemic control in adults with type 2 diabetes mellitus. (1)

Limitations of Use:

Not recommended for use to improve glycemic control in patients with type 1 diabetes mellitus. (1)

2 DOSAGE AND ADMINISTRATION

- Assess renal function prior to initiation and as clinically indicated. (2.1)
- Correct volume depletion before initiation. (2.1)
- Individualize the starting dosage based on the patient's current regimen. (2.2)
- Maximum recommended dosage is 7.5 mg ertugliflozin/1,000 mg metformin orally twice daily. (2.2)
- Take orally twice daily with meals, with gradual dose escalation. (2.2)
  - Do not use in patients with an estimated glomerular filtration rate (eGFR) below 30 mL/minute/1.73 m^2.
  - Use is not recommended in patients with an eGFR less than 45 mL/min/1.73 m^2. (2.2)
  - Use is contraindicated in patients with severe renal impairment (eGFR less than 30 mL/min/1.73 m^2), end stage-renal disease (ESRD), or on dialysis. (2.2)
- SEGLUROMET may need to be discontinued at time of, or prior to, iodinated contrast imaging procedures. (2.3)
- Withhold SEGLUROMET for at least 4 days, if possible, prior to surgery or procedures associated with prolonged fasting. (2.4)

3 DOSAGE FORMS AND STRENGTHS

Tablets:

- Ertugliflozin 2.5 mg and metformin hydrochloride 500 mg (3)
- Ertugliflozin 2.5 mg and metformin hydrochloride 1,000 mg (3)
- Ertugliflozin 7.5 mg and metformin hydrochloride 500 mg (3)
- Ertugliflozin 7.5 mg and metformin hydrochloride 1,000 mg (3)

4 CONTRAINDICATIONS

- Severe renal impairment (eGFR less than 30 mL/min/1.73 m^2), end stage-renal disease, or patients on dialysis. (4)
- Metabolic acidosis, including diabetic ketoacidosis. (4)
- Hypersensitivity to ertugliflozin, metformin or any excipient. (4)

5 WARNINGS AND PRECAUTIONS

- Lactic Acidosis: See boxed warning. (5.1)
- Diabetic Ketoacidosis in Patients with Type 1 Diabetes Mellitus and Other Ketoacidosis: Consider ketone monitoring in patients at risk for ketoacidosis, as indicated. Assess for ketoacidosis regardless of presenting blood glucose levels and discontinue SEGLUROMET if ketoacidosis is suspected. Monitor patients for resolution of ketoacidosis before restarting. (5.2)
- Lower Limb Amputation: Monitor patients for infections or ulcers of lower limbs, and discontinue if these occur. (5.3)
- Volume Depletion: May result in acute kidney injury. Before initiating, assess and correct volume status in patients with renal impairment, low systolic blood pressure, elderly patients, or patients on diuretics. Monitor for signs and symptoms during therapy. (5.4)
- Urosepsis and Pyelonephritis: Evaluate patients for signs and symptoms of urinary tract infections and treat promptly, if indicated. (5.5)
- Hypoglycemia: Consider a lower dose of insulin or insulin secretagogue to reduce risk of hypoglycemia when used in combination. (5.6)
- Necrotizing Fasciitis of the Perineum (Fournier's Gangrene): Serious, life-threatening cases have occurred in both females and males. Assess patients presenting with pain or tenderness, erythema, or swelling in the genital or perineal area, along with fever or malaise. If suspected, institute prompt treatment. (5.7)
- Genital Mycotic Infections: Monitor and treat if indicated. (5.8)
- Vitamin B12 Deficiency: Metformin may lower vitamin B12 levels. Measure hematological parameters annually. (5.9)

6 ADVERSE REACTIONS

- Most common adverse reactions associated with ertugliflozin (incidence ≥5%) were female genital mycotic infections. (6.1)
- Most common adverse reactions associated with metformin (incidence ≥5%) were diarrhea, nausea, vomiting, flatulence, abdominal discomfort, indigestion, asthenia, and headache. (6.1)

To report SUSPECTED ADVERSE REACTIONS, contact Merck Sharp & Dohme LLC at 1-877-888-4231 or FDA at 1-800-FDA-1088 or www.fda.gov/medwatch .

7 DRUG INTERACTIONS

- Carbonic Anhydrase Inhibitors: May increase risk of lactic acidosis. Consider more frequent monitoring. (7.2)
- Drugs that Reduce Metformin Clearance: May increase risk of lactic acidosis. Consider benefits and risks of concomitant use. (7.2)
- See full prescribing information for additional drug interactions and information on interference of SEGLUROMET with laboratory tests. (7)

8 USE IN SPECIFIC POPULATIONS

- Pregnancy: Advise females of the potential risk to a fetus, especially during the second and third trimesters. (8.1)
- Lactation: Breastfeeding not recommended. (8.2)
- Females and Males of Reproductive Potential: Advise premenopausal females of the potential for an unintended pregnancy. (8.3)
- Geriatrics: Higher incidence of adverse reactions related to reduced intravascular volume. (8.5)
- Renal impairment: Higher incidence of adverse reactions related to reduced intravascular volume and renal function. (8.6)
- Hepatic impairment: Avoid use in patients with hepatic impairment. (8.7)

FULL PRESCRIBING INFORMATION

WARNING: LACTIC ACIDOSIS

Postmarketing cases of metformin-associated lactic acidosis have resulted in death, hypothermia, hypotension, and resistant bradyarrhythmias. The onset of metformin-associated lactic acidosis is often subtle, accompanied only by nonspecific symptoms such as malaise, myalgias, respiratory distress, somnolence, and abdominal pain. Metformin-associated lactic acidosis was characterized by elevated blood lactate levels (>5 mmol/Liter), anion gap acidosis (without evidence of ketonuria or ketonemia), an increased lactate/pyruvate ratio, and metformin plasma levels generally >5 mcg/mL [see Warnings and Precautions (5.1)].

Risk factors for metformin-associated lactic acidosis include renal impairment, concomitant use of certain drugs (e.g., carbonic anhydrase inhibitors such as topiramate), age 65 years old or greater, having a radiological study with contrast, surgery and other procedures, hypoxic states (e.g., acute congestive heart failure), excessive alcohol intake, and hepatic impairment.

Steps to reduce the risk of and manage metformin-associated lactic acidosis in these high risk groups are provided in the Full Prescribing Information [see Dosage and Administration (2.2), Contraindications (4), Warnings and Precautions (5.1), Drug Interactions (7), and Use in Specific Populations (8.6, 8.7)].

If metformin-associated lactic acidosis is suspected, immediately discontinue SEGLUROMET and institute general supportive measures in a hospital setting. Prompt hemodialysis is recommended [see Warnings and Precautions (5.1)].

1 INDICATIONS AND USAGE

SEGLUROMET® is indicated as an adjunct to diet and exercise to improve glycemic control in adults with type 2 diabetes mellitus.

Limitations of Use

Not recommended for use to improve glycemic control in patients with type 1 diabetes mellitus [see Warnings and Precautions (5.2)].

2 DOSAGE AND ADMINISTRATION

2.1 Prior to Initiation of SEGLUROMET

- Assess renal function before initiating SEGLUROMET and as clinically indicated [see Warnings and Precautions (5.2)].
- Assess volume status. In patients with volume depletion, correct this condition before initiating SEGLUROMET [see Warnings and Precautions (5.4) and Use in Specific Populations (8.5, 8.6)].

2.2 Recommended Dosage

- Individualize the starting dosage of SEGLUROMET, ertugliflozin and metformin hydrochloride (HCI), based on the patient’s current regimen, while not exceeding the maximum recommended oral daily dosage of 15 mg ertugliflozin and 2,000 mg metformin HCl:
  - In patients on metformin HCI, switch to SEGLUROMET tablets containing 2.5 mg ertugliflozin, with a similar total oral daily dosage of metformin HCl.
  - In patients on ertugliflozin, switch to SEGLUROMET tablets containing 500 mg metformin HCl, with a similar total oral daily dosage of ertugliflozin.
  - In patients already treated with ertugliflozin and metformin HCl, switch to SEGLUROMET tablets containing the same total oral daily dosage of ertugliflozin and a similar daily dosage of metformin HCI.
- Take SEGLUROMET orally twice daily with meals, with gradual dosage escalation for those initiating metformin HCl to reduce the gastrointestinal side effects due to metformin [see Adverse Reactions (6.1)].
- Dosing may be adjusted based on effectiveness and tolerability.
- Use of SEGLUROMET is not recommended in patients with an estimated glomerular filtration rate (eGFR) less than 45 mL/min/1.73 m^2.
- Use of SEGLUROMET is contraindicated in patients with severe renal impairment (eGFR less than 30 mL/min/1.73 m^2), end stage-renal disease (ESRD), or on dialysis [see Contraindications (4)].

2.3 Discontinuation for Iodinated Contrast Imaging Procedures

Discontinue SEGLUROMET at the time of, or prior to, an iodinated contrast imaging procedure in patients with an eGFR less than 60 mL/min/1.73 m^2; in patients with a history of liver disease, alcoholism or heart failure; or in patients who will be administered intra-arterial iodinated contrast. Re-evaluate eGFR 48 hours after the imaging procedure; restart SEGLUROMET if renal function is stable [see Warnings and Precautions (5.1)].

2.4 Temporary Interruption for Surgery

Withhold SEGLUROMET for at least 4 days, if possible, prior to surgery or procedures associated with prolonged fasting. Resume SEGLUROMET when the patient is clinically stable and has resumed oral intake [see Warnings and Precautions (5.2) and Clinical Pharmacology (12.2)].

3 DOSAGE FORMS AND STRENGTHS

- Tablets: ertugliflozin 2.5 mg and metformin HCl 500 mg, pink, oval, debossed with "2.5/500" on one side and plain on the other side.
- Tablets: ertugliflozin 2.5 mg and metformin HCl 1,000 mg, pink, oval, debossed with "2.5/1000" on one side and plain on the other side.
- Tablets: ertugliflozin 7.5 mg and metformin HCl 500 mg, red, oval, debossed with "7.5/500" on one side and plain on the other side.
- Tablets: ertugliflozin 7.5 mg and metformin HCl 1,000 mg, red, oval, debossed with "7.5/1000" on one side and plain on the other side.

4 CONTRAINDICATIONS

SEGLUROMET is contraindicated in patients with:

- Hypersensitivity to ertugliflozin, metformin, or any excipient in SEGLUROMET. Reactions such as angioedema or anaphylaxis have occurred [see Adverse Reactions (6.2)].
- Severe renal impairment (eGFR less than 30 mL/min/1.73 m^2), end stage-renal disease (ESRD), or on dialysis [see Use in Specific Populations (8.6)].
- Acute or chronic metabolic acidosis, including diabetic ketoacidosis, with or without coma.

5 WARNINGS AND PRECAUTIONS

5.1 Lactic Acidosis

There have been postmarketing cases of metformin-associated lactic acidosis, including fatal cases. These cases had a subtle onset and were accompanied by nonspecific symptoms such as malaise, myalgias, abdominal pain, respiratory distress, or increased somnolence; however, hypothermia, hypotension and resistant bradyarrhythmias have occurred with severe acidosis. Metformin-associated lactic acidosis was characterized by elevated blood lactate concentrations (>5 mmol/Liter), anion gap acidosis (without evidence of ketonuria or ketonemia), and an increased lactate: pyruvate ratio; metformin plasma levels were generally >5 mcg/mL. Metformin decreases liver uptake of lactate increasing lactate blood levels which may increase the risk of lactic acidosis, especially in patients at risk.

If metformin-associated lactic acidosis is suspected, general supportive measures should be instituted promptly in a hospital setting, along with immediate discontinuation of SEGLUROMET. In SEGLUROMET-treated patients with a diagnosis or strong suspicion of lactic acidosis, prompt hemodialysis is recommended to correct the acidosis and remove accumulated metformin (metformin hydrochloride is dialyzable, with a clearance of up to 170 mL/minute under good hemodynamic conditions). Hemodialysis has often resulted in reversal of symptoms and recovery.

Educate patients and their families about the symptoms of lactic acidosis and if these symptoms occur instruct them to discontinue SEGLUROMET and report these symptoms to their healthcare provider.

For each of the known and possible risk factors for metformin-associated lactic acidosis, recommendations to reduce the risk of and manage metformin-associated lactic acidosis are provided below:

Renal Impairment: The postmarketing metformin-associated lactic acidosis cases primarily occurred in patients with significant renal impairment. The risk of metformin accumulation and metformin-associated lactic acidosis increases with the severity of renal impairment because metformin is substantially excreted by the kidney [see Warnings and Precautions (5.4) and Clinical Pharmacology (12.3)].

- Before initiating SEGLUROMET, obtain an eGFR.
- Use of SEGLUROMET is not recommended in patients with an eGFR less than 45 mL/min/1.73 m^2.
- SEGLUROMET is contraindicated in patients with severe renal impairment (an eGFR less than 30 mL/min/1.73 m^2), end stage-renal disease (ESRD), or on dialysis.
- Obtain an eGFR at least annually in all patients taking SEGLUROMET. In patients at increased risk for the development of renal impairment (e.g., the elderly), renal function should be assessed more frequently.

Drug Interactions: The concomitant use of SEGLUROMET with specific drugs may increase the risk of metformin-associated lactic acidosis: those that impair renal function, result in significant hemodynamic change, interfere with acid-base balance or increase metformin accumulation (e.g., cationic drugs) [see Drug Interactions (7)]. Therefore, consider more frequent monitoring of patients.

Age 65 or Greater: The risk of metformin-associated lactic acidosis increases with the patient's age because elderly patients have a greater likelihood of having hepatic, renal, or cardiac impairment than younger patients. Assess renal function more frequently in elderly patients [see Use in Specific Populations (8.5)].

Radiological Studies with Contrast: Administration of intravascular iodinated contrast agents in metformin-treated patients has led to an acute decrease in renal function and the occurrence of lactic acidosis. Stop SEGLUROMET at the time of, or prior to, an iodinated contrast imaging procedure in patients with an eGFR less than 60 mL/min/1.73 m^2; in patients with a history of hepatic impairment, alcoholism, or heart failure; or in patients who will be administered intra-arterial iodinated contrast. Re-evaluate eGFR 48 hours after the imaging procedure, and restart SEGLUROMET if renal function is stable.

Surgery and Other Procedures: Withholding of food and fluids during surgical or other procedures may increase the risk for volume depletion, hypotension and renal impairment. SEGLUROMET should be temporarily discontinued while patients have restricted food and fluid intake.

Hypoxic States: Several of the postmarketing cases of metformin-associated lactic acidosis occurred in the setting of acute congestive heart failure (particularly when accompanied by hypoperfusion and hypoxemia). Cardiovascular collapse (shock), acute myocardial infarction, sepsis, and other conditions associated with hypoxemia have been associated with lactic acidosis and may also cause pre-renal azotemia. When such events occur, discontinue SEGLUROMET.

Excessive Alcohol Intake: Alcohol potentiates the effect of metformin on lactate metabolism and this may increase the risk of metformin-associated lactic acidosis. Warn patients against excessive alcohol intake while receiving SEGLUROMET.

Hepatic Impairment: Patients with hepatic impairment have developed metformin-associated lactic acidosis. This may be due to impaired lactate clearance resulting in higher lactate blood levels. Therefore, avoid use of SEGLUROMET in patients with clinical or laboratory evidence of hepatic disease.

5.2 Diabetic Ketoacidosis in Patients with Type 1 Diabetes Mellitus and Other Ketoacidosis

In patients with type 1 diabetes mellitus, SEGLUROMET significantly increases the risk of diabetic ketoacidosis, a life-threatening event, beyond the background rate. In placebo-controlled trials of patients with type 1 diabetes mellitus, the risk of ketoacidosis was markedly increased in patients who received sodium glucose transporter 2 (SGLT2) inhibitors compared to patients who received placebo; this risk may be greater with higher doses. SEGLUROMET is not indicated for glycemic control in patients with type 1 diabetes mellitus.

Type 2 diabetes mellitus and pancreatic disorders (e.g., history of pancreatitis or pancreatic surgery) are also risk factors for ketoacidosis. There have been postmarketing reports of fatal events of ketoacidosis in patients with type 2 diabetes mellitus using SGLT2 inhibitors.

Precipitating conditions for diabetic ketoacidosis or other ketoacidosis include under-insulinization due to insulin dose reduction or missed insulin doses, acute febrile illness, reduced caloric intake, ketogenic diet, surgery, volume depletion, and alcohol abuse.

Signs and symptoms are consistent with dehydration and severe metabolic acidosis and include nausea, vomiting, abdominal pain, generalized malaise, and shortness of breath. Blood glucose levels at presentation may be below those typically expected for diabetic ketoacidosis (e.g., less than 250 mg/dL). Ketoacidosis and glucosuria may persist longer than typically expected. Urinary glucose excretion persists for 4 days after discontinuing SEGLUROMET [see Clinical Pharmacology (12.2)]; however, there have been postmarketing reports of ketoacidosis and/or glucosuria lasting greater than 6 days and some up to 2 weeks after discontinuation of SGLT2 inhibitors.

Consider ketone monitoring in patients at risk for ketoacidosis if indicated by the clinical situation. Assess for ketoacidosis regardless of presenting blood glucose levels in patients who present with signs and symptoms consistent with severe metabolic acidosis. If ketoacidosis is suspected, discontinue SEGLUROMET, promptly evaluate, and treat ketoacidosis, if confirmed. Monitor patients for resolution of ketoacidosis before restarting SEGLUROMET.

Withhold SEGLUROMET, if possible, in temporary clinical situations that could predispose patients to ketoacidosis. Resume SEGLUROMET when the patient is clinically stable and has resumed oral intake [see Dosage and Administration (2.4)].

Educate all patients on the signs and symptoms of ketoacidosis and instruct patients to discontinue SEGLUROMET and seek medical attention immediately if signs and symptoms occur.

5.3 Lower Limb Amputation

In a long-term cardiovascular outcomes study [see Clinical Studies (14.2)], in patients with type 2 diabetes mellitus and established cardiovascular disease, the occurrence of non-traumatic lower limb amputations was reported with event rates of 4.7, 5.7, and 6.0 events per 1,000 patient-years in the placebo, ertugliflozin 5 mg, and ertugliflozin 15 mg treatment arms, respectively.

Amputation of the toe and foot were most frequent (81 out of 109 patients with lower limb amputations). Some patients had multiple amputations, some involving both lower limbs.

Lower limb infections, gangrene, and diabetic foot ulcers were the most common precipitating medical events leading to the need for an amputation. Patients with amputations were more likely to be male, have higher A1C (%) at baseline, have a history of peripheral arterial disease, amputation or peripheral revascularization procedure, diabetic foot, and to have been taking diuretics or insulin.

Across seven ertugliflozin clinical trials, non-traumatic lower limb amputations were reported in 1 (0.1%) patient in the comparator group, 3 (0.2%) patients in the ertugliflozin 5 mg group, and 8 (0.5%) patients in the ertugliflozin 15 mg group.

Monitor patients receiving SEGLUROMET for signs and symptoms of infection (including osteomyelitis), new pain or tenderness, sores or ulcers involving the lower limbs, and discontinue SEGLUROMET if these complications occur.

5.4 Volume Depletion

SEGLUROMET can cause intravascular volume contraction which may sometimes manifest as symptomatic hypotension or acute transient changes in creatinine [see Adverse Reactions (6.1)]. There have been postmarketing reports of acute kidney injury, some requiring hospitalization and dialysis, in patients with type 2 diabetes mellitus receiving SGLT2 inhibitors, including SEGLUROMET. Patients with impaired renal function (eGFR less than 60 mL/min/1.73 m^2) [see Use in Specific Populations (8.6)], elderly patients, patients with low systolic blood pressure, or patients on loop diuretics may be at increased risk for volume depletion or hypotension. Before initiating SEGLUROMET in patients with one or more of these characteristics, assess volume status and renal function. In patients with volume depletion, correct this condition before initiating SEGLUROMET. Monitor for signs and symptoms of volume depletion, and renal function after initiating therapy.

5.5 Urosepsis and Pyelonephritis

There have been postmarketing reports of serious urinary tract infections, including urosepsis and pyelonephritis, requiring hospitalization in patients receiving medicines containing SGLT2 inhibitors. Treatment with medicines containing SGLT2 inhibitors increases the risk for urinary tract infections. Evaluate patients for signs and symptoms of urinary tract infections and treat promptly, if indicated [see Adverse Reactions (6)].

5.6 Hypoglycemia with Concomitant Use with Insulin or Insulin Secretagogues

Insulin and insulin secretagogues (e.g., sulfonylurea) are known to cause hypoglycemia. SEGLUROMET may increase the risk of hypoglycemia when used in combination with insulin or an insulin secretagogue [see Adverse Reactions (6.1)]. The risk of hypoglycemia may be lowered by a reduction in the dose of insulin or sulfonylurea (or other concomitantly administered insulin secretagogues). Inform patients using these medications concomitantly of this risk and educate them on the signs and symptoms of hypoglycemia.

5.7 Necrotizing Fasciitis of the Perineum (Fournier's Gangrene)

Reports of necrotizing fasciitis of the perineum (Fournier’s Gangrene), a rare but serious and life-threatening necrotizing infection requiring urgent surgical intervention, have been identified in postmarketing surveillance in patients with diabetes mellitus receiving SGLT2 inhibitors, including ertugliflozin. Cases have been reported in females and males. Serious outcomes have included hospitalization, multiple surgeries, and death.

Patients treated with SEGLUROMET presenting with pain or tenderness, erythema, or swelling in the genital or perineal area, along with fever or malaise, should be assessed for necrotizing fasciitis. If suspected, start treatment immediately with broad-spectrum antibiotics and, if necessary, surgical debridement. Discontinue SEGLUROMET, closely monitor blood glucose levels, and provide appropriate alternative therapy for glycemic control.

5.8 Genital Mycotic Infections

Ertugliflozin increases the risk of genital mycotic infections. Patients who have a history of genital mycotic infections or who are uncircumcised are more likely to develop genital mycotic infections [see Adverse Reactions (6.1)]. Monitor and treat appropriately.

5.9 Vitamin B12 Deficiency

In metformin clinical trials of 29-week duration, a decrease to subnormal levels of previously normal serum vitamin B12 levels was observed in approximately 7% of patients. Such decrease, possibly due to interference with B12 absorption from the B12-intrinsic factor complex, may be associated with anemia but appears to be rapidly reversible with discontinuation of metformin or vitamin B12 supplementation. Certain individuals (those with inadequate vitamin B12 or calcium intake or absorption) appear to be predisposed to developing subnormal vitamin B12 levels. Measure hematologic parameters on an annual basis and vitamin B12 at 2 to 3 year intervals in patients on metformin and manage any abnormalities [see Adverse Reactions (6.1)].

6 ADVERSE REACTIONS

The following important adverse reactions are described elsewhere in the labeling:

- Lactic Acidosis [see Boxed Warning and Warnings and Precautions (5.1)]
- Diabetic Ketoacidosis in Patients with Type 1 Diabetes and Other Ketoacidosis [see Warnings and Precautions (5.2)]
- Lower Limb Amputation [see Warnings and Precautions (5.3)]
- Volume Depletion [see Warnings and Precautions (5.4)]
- Urosepsis and Pyelonephritis [see Warnings and Precautions (5.5)]
- Hypoglycemia with Concomitant Use with Insulin or Insulin Secretagogues [see Warnings and Precautions (5.6)]
- Necrotizing Fasciitis of the Perineum (Fournier's Gangrene) [see Warnings and Precautions (5.7)]
- Genital Mycotic Infections [see Warnings and Precautions (5.8)]
- Vitamin B12 Deficiency [see Warnings and Precautions (5.9)]

6.1 Clinical Trials Experience

Because clinical trials are conducted under widely varying conditions, adverse reaction rates observed in the clinical trials of a drug cannot be directly compared to rates in the clinical trials of another drug and may not reflect the rates observed in practice.

Ertugliflozin and Metformin Hydrochloride

The incidence and type of adverse reactions in the two 26-week, placebo-controlled trials of ertugliflozin 5 mg and 15 mg added to metformin HCl, representing a majority of data from the three 26-week, placebo-controlled trials, were similar to the adverse reactions described in Table 1.

Ertugliflozin

Pool of Placebo-Controlled Trials

The data in Table 1 are derived from a pool of three 26-week, placebo-controlled trials. Ertugliflozin was used as monotherapy in one trial and as add-on therapy in two trials [see Clinical Studies (14)]. These data reflect exposure of 1,029 patients to ertugliflozin with a mean exposure duration of approximately 25 weeks. Patients received ertugliflozin 5 mg (N=519), ertugliflozin 15 mg (N=510), or placebo (N=515) once daily. The mean age of the population was 57 years and 2% were older than 75 years of age. Fifty-three percent (53%) of the population was male and 73% were White, 15% were Asian, and 7% were Black or African American. At baseline the population had diabetes for an average of 7.5 years, had a mean HbA1c of 8.1%, and 19.4% had established microvascular complications of diabetes. Baseline renal function (mean eGFR 88.9 mL/min/1.73 m^2) was normal or mildly impaired in 97% of patients and moderately impaired in 3% of patients.

Table 1 shows common adverse reactions associated with the use of ertugliflozin. These adverse reactions were not present at baseline, occurred more commonly on ertugliflozin than on placebo, and occurred in at least 2% of patients treated with either ertugliflozin 5 mg or ertugliflozin 15 mg.

Table 1: Adverse Reactions Reported in ≥2% of Patients with Type 2 Diabetes Mellitus Treated with Ertugliflozin [The three placebo-controlled studies included one monotherapy trial and two add-on combination trials with metformin HCl or with metformin HCl and sitagliptin.] and Greater than Placebo in Pooled Placebo-Controlled Clinical Studies of Ertugliflozin Monotherapy or Combination Therapy
 | Number (%) of Patients
 | Placebo N = 515 | Ertugliflozin 5 mg N = 519 | Ertugliflozin 15 mg N = 510
Female genital mycotic infections [Includes: genital candidiasis, genital infection fungal, vaginal infection, vulvitis, vulvovaginal candidiasis, vulvovaginal mycotic infection, and vulvovaginitis. Percentages calculated with the number of female patients in each group as denominator: placebo (N=235), ertugliflozin 5 mg (N=252), ertugliflozin 15 mg (N=245).] | 3.0% | 9.1% | 12.2%
Male genital mycotic infections [Includes: balanitis candida, balanoposthitis, genital infection, and genital infection fungal. Percentages calculated with the number of male patients in each group as denominator: placebo (N=280), ertugliflozin 5 mg (N=267), ertugliflozin 15 mg (N=265).] | 0.4% | 3.7% | 4.2%
Urinary tract infections [Includes: cystitis, dysuria, streptococcal urinary tract infection, urethritis, urinary tract infection.] | 3.9% | 4.0% | 4.1%
Headache | 2.3% | 3.5% | 2.9%
Vaginal pruritus [Includes: vulvovaginal pruritus and pruritus genital. Percentages calculated with the number of female patients in each group as denominator: placebo (N=235), ertugliflozin 5 mg (N=252), ertugliflozin 15 mg (N=245).] | 0.4% | 2.8% | 2.4%
Increased urination [Includes: pollakiuria, micturition urgency, polyuria, urine output increased, and nocturia.] | 1.0% | 2.7% | 2.4%
Nasopharyngitis | 2.3% | 2.5% | 2.0%
Back pain | 2.3% | 1.7% | 2.5%
Weight decreased | 1.0% | 1.2% | 2.4%
Thirst [Includes: thirst, dry mouth, polydipsia, and dry throat.] | 0.6% | 2.7% | 1.4%

Volume Depletion

Ertugliflozin causes an osmotic diuresis, which may lead to intravascular volume contraction and adverse reactions related to volume depletion, particularly in patients with impaired renal function (eGFR less than 60 mL/min/1.73 m^2). In patients with moderate renal impairment, adverse reactions related to volume depletion (e.g., dehydration, dizziness postural, presyncope, syncope, hypotension, and orthostatic hypotension) were reported in 0%, 4.4%, and 1.9% of patients treated with placebo, ertugliflozin 5 mg, and ertugliflozin 15 mg, respectively. Ertugliflozin may also increase the risk of hypotension in other patients at risk for volume contraction [see Use in Specific Populations (8.5, 8.6)].

Hypoglycemia

The incidence of hypoglycemia by study is shown in Table 2.

Table 2: Incidence of Overall [Overall hypoglycemic events: plasma or capillary glucose of less than or equal to 70 mg/dL.] and Severe [Severe hypoglycemic events: required assistance, lost consciousness, or experienced a seizure regardless of blood glucose.] Hypoglycemia in Placebo-Controlled Clinical Studies in Patients with Type 2 Diabetes Mellitus
Add-on Combination Therapy with Metformin HCl (26 weeks) | Placebo (N = 209) | Ertugliflozin 5 mg (N = 207) | Ertugliflozin 15 mg (N = 205)
Overall [N (%)] | 9 (4.3) | 15 (7.2) | 16 (7.8)
Severe [N (%)] | 1 (0.5) | 1 (0.5) | 0 (0.0)
Add-on Combination Therapy with Metformin HCl and Sitagliptin (26 weeks) | Placebo (N = 153) | Ertugliflozin 5 mg (N = 156) | Ertugliflozin 15 mg (N = 153)
Overall [N (%)] | 5 (3.3) | 7 (4.5) | 3 (2.0)
Severe [N (%)] | 1 (0.7) | 1 (0.6) | 0 (0.0)
Add-on Combination with Insulin with or without Metformin HCl (18 weeks) | Placebo (N = 347) | Ertugliflozin 5 mg (N = 348) | Ertugliflozin 15 mg (N = 370)
Overall [N (%)] | 130 (37.5) | 137 (39.4) | 144 (38.9)
Severe [N (%)] | 12 (3.5) | 13 (3.7) | 19 (5.1)
Add-on Combination with Metformin HCl and a Sulfonylurea (18 weeks) | Placebo (N = 117) | Ertugliflozin 5 mg (N = 100) | Ertugliflozin 15 mg (N = 113)
Overall [N (%)] | 17 (14.5) | 20 (20.0) | 30 (26.5)
Severe [N (%)] | 1 (0.9) | 2 (2.0) | 2 (1.8)

Lower Limb Amputation

In a long-term cardiovascular outcomes study [see Clinical Studies (14.2)], in patients with type 2 diabetes mellitus and established cardiovascular disease, the occurrence of non-traumatic lower limb amputations was reported with event rates of 4.7, 5.7, and 6.0 events per 1,000 patient-years in the placebo, ertugliflozin 5 mg, and ertugliflozin 15 mg treatment arms, respectively.

Across seven ertugliflozin clinical trials, non-traumatic lower limb amputations were reported in 1 (0.1%) patient in the comparator group, 3 (0.2%) patients in the ertugliflozin 5 mg group, and 8 (0.5%) patients in the ertugliflozin 15 mg group.

Genital Mycotic Infections

In the pool of three placebo-controlled clinical trials, the incidence of female genital mycotic infections (e.g., genital candidiasis, genital infection fungal, vaginal infection, vulvitis, vulvovaginal candidiasis, vulvovaginal mycotic infection, vulvovaginitis) occurred in 3%, 9.1%, and 12.2%, of females treated with placebo, ertugliflozin 5 mg, and ertugliflozin 15 mg, respectively (see Table 1). In females, discontinuation due to genital mycotic infections occurred in 0% and 0.6% of patients treated with placebo and ertugliflozin, respectively.

In the same pool, male genital mycotic infections (e.g., balanitis candida, balanoposthitis, genital infection, genital infection fungal) occurred in 0.4%, 3.7%, and 4.2% of males treated with placebo, ertugliflozin 5 mg, and ertugliflozin 15 mg, respectively. Male genital mycotic infections occurred more commonly in uncircumcised males. In males, discontinuations due to genital mycotic infections occurred in 0% and 0.2% of patients treated with placebo and ertugliflozin, respectively. Phimosis was reported in 8 of 1,729 (0.5%) male ertugliflozin-treated patients, of which four required circumcision.

Urinary Tract Infections

In VERTIS CV urinary tract infections (e.g., urinary tract infection, cystitis, dysuria) occurred in 10.2%, 12.2% and 12.0% of patients treated with placebo, ertugliflozin 5 mg and ertugliflozin 15 mg, respectively. The incidences of serious urinary tract infections were 0.8%, 0.9% and 0.4% with placebo, ertugliflozin 5 mg and ertugliflozin 15 mg, respectively.

Metformin HCl

The most common (5% or greater incidence) established adverse reactions due to initiation of metformin HCl therapy are diarrhea, nausea, vomiting, flatulence, abdominal discomfort, indigestion, asthenia, and headache.

In controlled clinical trials of metformin HCl of 29 weeks duration, a decrease to subnormal levels of previously normal serum vitamin B12 levels was observed in approximately 7% of patients.

Laboratory Tests

Ertugliflozin

Changes in Serum Creatinine and eGFR

Initiation of ertugliflozin causes an increase in serum creatinine and decrease in eGFR within weeks of starting therapy and then these changes stabilize. In a study of patients with moderate renal impairment, larger mean changes were observed. In a long-term cardiovascular outcomes trial, an initial increase in serum creatinine and a decrease in eGFR within weeks of starting therapy was observed (at Week 6 eGFR changes of -2.7, -3.8 and -0.4 mL/min/1.73 m^2 in the ertugliflozin 5 mg, ertugliflozin 15 mg and placebo arms, respectively). The initial decline was followed by a recovery toward baseline to Week 52 (eGFR change from baseline of - 0.4, - 1.1 and - 0.2 mL/min/1.73 m^2 in ertugliflozin 5 mg, ertugliflozin 15 mg, and placebo arms, respectively). Acute hemodynamic changes may play a role in the early renal function changes observed with ertugliflozin since they are reversed after treatment discontinuation.

Increases in Low-Density Lipoprotein Cholesterol (LDL-C)

In the pool of three placebo-controlled trials, dose-related increases in LDL-C were observed in patients treated with ertugliflozin. Mean percent changes from baseline to Week 26 in LDL-C relative to placebo were 2.6% and 5.4% with ertugliflozin 5 mg and ertugliflozin 15 mg, respectively. The range of mean baseline LDL-C was 96.6 to 97.7 mg/dL across treatment groups.

Increases in Hemoglobin

In the pool of three placebo-controlled trials, mean changes (percent changes) from baseline to Week 26 in hemoglobin were -0.21 g/dL (-1.4%) with placebo, 0.46 g/dL (3.5%) with ertugliflozin 5 mg, and 0.48 g/dL (3.5%) with ertugliflozin 15 mg. The range of mean baseline hemoglobin was 13.90 to 14.00 g/dL across treatment groups. At the end of treatment, 0.0%, 0.2%, and 0.4% of patients treated with placebo, ertugliflozin 5 mg, and ertugliflozin 15 mg, respectively, had a hemoglobin increase greater than 2 g/dL and above the upper limit of normal.

Increases in Serum Phosphate

In the pool of three placebo-controlled trials, mean changes (percent changes) from baseline in serum phosphate were 0.04 mg/dL (1.9%) with placebo, 0.21 mg/dL (6.8%) with ertugliflozin 5 mg, and 0.26 mg/dL (8.5%) with ertugliflozin 15 mg. The range of mean baseline serum phosphate was 3.53 to 3.54 mg/dL across treatment groups. In a clinical trial of patients with moderate renal impairment, mean changes (mean percent changes) from baseline at Week 26 in serum phosphate were -0.01 mg/dL (0.8%) with placebo, 0.29 mg/dL (9.7%) with ertugliflozin 5 mg, and 0.24 mg/dL (7.8%) with ertugliflozin 15 mg.

6.2 Postmarketing Experience

Additional adverse reactions have been identified during post approval use of ertugliflozin, metformin HCl, both components of SEGLUROMET. Because these reactions are reported voluntarily from a population of uncertain size, it is generally not possible to reliably estimate their frequency or establish a causal relationship to drug exposure.

Ertugliflozin

- Infections: necrotizing fasciitis of the perineum (Fournier’s Gangrene)
- Skin and Subcutaneous Tissue Disorders: angioedema, rash

Metformin HCl

- Hepatobiliary Disorders: cholestatic, hepatocellular, and mixed hepatocellular liver injury

7 DRUG INTERACTIONS

Table 3: Clinically Significant Drug Interactions with SEGLUROMET
Carbonic Anhydrase Inhibitors
Clinical Impact: | The risk of lactic acidosis may increase due to concomitant use of Topiramate or other carbonic anhydrase inhibitors (e.g., zonisamide, acetazolamide or dichlorphenamide) with metformin. These drugs frequently cause a decrease in serum bicarbonate and induce non-anion gap, hyperchloremic metabolic acidosis.
Intervention: | more frequent monitoring of these patients.
Drugs that Reduce Metformin Clearance
Clinical Impact: | The risk of lactic acidosis may increase due to concomitant use of drugs that interfere with common renal tubular transport systems involved in the renal elimination of metformin (e.g., organic cationic transporter-2 [OCT2] / multidrug and toxin extrusion [MATE] inhibitors such as ranolazine, vandetanib, dolutegravir, and cimetidine) which increase systemic exposure to metformin
Intervention | Consider the benefits and risks of concomitant use.
Alcohol
Clinical Impact: | Potentiate the effect of metformin on lactate metabolism.
Intervention: | Warn patients against excessive alcohol intake while receiving SEGLUROMET.
Insulin or Insulin Secretagogues
Clinical Impact: | The risk of hypoglycemia is increased when ertugliflozin is used in combination with insulin or an insulin secretagogue.
Intervention: | A lower dose of insulin or insulin secretagogue may be required to minimize the risk of hypoglycemia when used in combination with SEGLUROMET.
Drugs that Affect Glycemic Control
Clinical Impact: | Certain drugs tend to produce hyperglycemia and may lead to loss of glycemic control. These drugs include the thiazides and other diuretics, corticosteroids, phenothiazines, thyroid products, estrogens, oral contraceptives, phenytoin, nicotinic acid, sympathomimetics, calcium channel blocking drugs, and isoniazid.
Intervention: | When a patient is receiving SEGLUROMET along with such drugs, the patient should be closely observed to maintain adequate glycemic control.
Lithium
Clinical Impact: | Concomitant use of an SGLT2 inhibitor with lithium may decrease serum lithium concentrations.
Intervention: | Monitor serum lithium concentration more frequently during SEGLUROMET initiation and dosage changes.
Positive Urine Glucose Test
Clinical Impact: | SGLT2 inhibitors increase urinary glucose excretion and will lead to positive urine glucose tests.
Intervention: | Monitoring glycemic control with urine glucose tests is not recommended in patients taking SEGLUROMET. Use alternative methods to monitor glycemic control.
Interference with 1,5-anhydroglucitol (1,5-AG) Assay
Clinical Impact: | Measurements of 1,5-AG are unreliable in assessing glycemic control in patients taking SGLT2 inhibitors.
Intervention: | Monitoring glycemic control with 1,5-AG assay is not recommended. Use alternative methods to monitor glycemic control.

8 USE IN SPECIFIC POPULATIONS

8.1 Pregnancy

Risk Summary

Based on animal data showing adverse renal effects, from ertugliflozin, SEGLUROMET is not recommended during the second and third trimesters of pregnancy. Published studies with metformin use during pregnancy have not reported a clear association with metformin and major birth defect or miscarriage risk (see Data).

The limited available data with SEGLUROMET in pregnant women are not sufficient to determine a drug-associated risk for major birth defects or miscarriage. There are risks to the mother and fetus associated with poorly controlled diabetes in pregnancy (see Clinical Considerations).

In animal studies, adverse renal changes were observed in rats when ertugliflozin was administered during a period of renal development corresponding to the late second and third trimesters of human pregnancy. Doses approximately 13 times the maximum clinical dose caused renal pelvic and tubule dilatations and renal mineralization that were not fully reversible. There was no evidence of fetal harm in rats or rabbits at exposures of ertugliflozin approximately 300 times higher than the maximal clinical dose of 15 mg/day when administered during organogenesis (see Data).

The estimated background risk of major birth defects is 6-10% in women with pre-gestational diabetes with a HbA1c >7 and has been reported to be as high as 20-25% in women with HbA1c >10. The estimated background risk of miscarriage for the indicated population is unknown. In the U.S. general population, the estimated background risk of major birth defects and miscarriage in clinically recognized pregnancies is 2-4% and 15-20%, respectively.

Clinical Considerations

Disease-Associated Maternal and/or Embryo/Fetal Risk

Poorly controlled diabetes in pregnancy increases the maternal risk for diabetic ketoacidosis, pre-eclampsia, spontaneous abortions, preterm delivery, and delivery complications. Poorly controlled diabetes increases the fetal risk for major birth defects, stillbirth, and macrosomia related morbidity.

Data

Human Data

Published data from postmarketing studies have not reported a clear association with metformin and major birth defects, miscarriage, or adverse maternal or fetal outcomes when metformin was used during pregnancy. However, these studies cannot definitely establish the absence of any metformin-associated risk because of methodological limitations, including small sample size and inconsistent comparator groups.

Animal Data

Ertugliflozin

When ertugliflozin was orally administered to juvenile rats from PND 21 to PND 90, increased kidney weight, renal tubule and renal pelvis dilatation, and renal mineralization occurred at doses greater than or equal to 5 mg/kg (13-fold human exposures, based on AUC). These effects occurred with drug exposure during periods of renal development in rats that correspond to the late second and third trimester of human renal development, and did not fully reverse within a 1-month recovery period.

In embryo-fetal development studies, ertugliflozin (50, 100 and 250 mg/kg/day) was administered orally to rats on gestation days 6 to 17 and to rabbits on gestation days 7 to 19. Ertugliflozin did not adversely affect developmental outcomes in rats and rabbits at maternal exposures that were approximately 300 times the human exposure at the maximum clinical dose of 15 mg/day, based on AUC. A maternally toxic dose (250 mg/kg/day) in rats (707 times the clinical dose) was associated with reduced fetal viability and a higher incidence of a visceral malformation (membranous ventricular septal defect). In the pre- and post-natal development study in pregnant rats, ertugliflozin was administered to the dams from gestation day 6 through lactation day 21 (weaning). Decreased post-natal growth (weight gain) was observed at maternal doses ≥100 mg/kg/day (greater than or equal to 331 times the human exposure at the maximum clinical dose of 15 mg/day, based on AUC).

Metformin HCl

Metformin did not adversely affect development outcomes when administered to rats and rabbits at doses up to 600 mg/kg/day. This represents an exposure of about 2 and 6 times the maximum recommended human dose of 2,000 mg based on body surface area comparisons for rats and rabbits, respectively. Determination of fetal concentrations demonstrated a partial placental barrier to metformin.

8.2 Lactation

Risk Summary

There is no information regarding the presence of SEGLUROMET or ertugliflozin in human milk, the effects on the breastfed infant, or the effects on milk production. Limited published studies report that metformin is present in human milk (see Data). However, there is insufficient information on the effects of metformin on the breastfed infant and no available information on the effects of metformin on milk production. Ertugliflozin (see Data) and metformin are present in the milk of lactating rats. Since human kidney maturation occurs in utero and during the first 2 years of life when lactational exposure may occur, there may be risk to the developing human kidney, based on data with ertugliflozin. Because of the potential for serious adverse reactions in a breastfed infant, advise women that the use of SEGLUROMET is not recommended while breastfeeding.

Data

The lacteal excretion of radiolabeled ertugliflozin in lactating rats was evaluated 10 to 12 days after parturition. Ertugliflozin derived radioactivity exposure in milk and plasma were similar, with a milk/plasma ratio of 1.07, based on AUC. Juvenile rats directly exposed to ertugliflozin during a developmental period corresponding to human kidney maturation were associated with a risk to the developing kidney (persistent increased organ weight, renal mineralization, and renal pelvic and tubular dilatations).

Published clinical lactation studies report that metformin is present in human milk, which resulted in infant doses approximately 0.11% to 1% of the maternal weight-adjusted dosage and a milk/plasma ratio ranging between 0.13 and 1. However, the studies were not designed to definitely establish the risk of use of metformin during lactation because of small sample size and limited adverse event data collected in infants.

8.3 Females and Males of Reproductive Potential

Discuss the potential for unintended pregnancy with premenopausal women as therapy with metformin may result in ovulation in some anovulatory women.

8.4 Pediatric Use

Safety and effectiveness of SEGLUROMET in pediatric patients under 18 years of age have not been established.

8.5 Geriatric Use

SEGLUROMET

No dosage adjustment of SEGLUROMET is recommended based on age. Elderly patients are more likely to have decreased renal function. Because renal function abnormalities can occur after initiating ertugliflozin, and metformin is known to be substantially excreted by the kidneys, care should be taken in dose selection in the elderly. Assess renal function in elderly patients prior to initiating dosing and periodically thereafter [see Dosage and Administration (2.1) and Warnings and Precautions (5.1, 5.4)].

Ertugliflozin

In ertugliflozin clinical trials, a total of 876 (25.7%) patients treated with ertugliflozin were 65 years and older, and 152 (4.5%) patients treated with ertugliflozin were 75 years and older. Patients 65 years and older had a higher incidence of adverse reactions related to volume depletion compared to younger patients; events were reported in 1.1%, 2.2%, and 2.6% of patients treated with comparator, ertugliflozin 5 mg, and ertugliflozin 15 mg, respectively [see Warnings and Precautions (5.4) and Adverse Reactions (6.1)].

In VERTIS CV, a total of 2780 (50.5%) patients treated with ertugliflozin were 65 years and older, and 595 (10.8%) patients treated with ertugliflozin were 75 years and older. Safety and efficacy were generally similar for patients age 65 years and older compared to patients younger than 65.

Metformin HCl

Controlled clinical studies of metformin did not include sufficient numbers of elderly patients to determine whether they respond differently from younger patients, although other reported clinical experience has not identified differences in responses between the elderly and young patients. In general, dose selection for an elderly patient should be cautious, usually starting at the low end of the dosing range, reflecting the greater frequency of decreased hepatic, renal, or cardiac function, and of concomitant disease or other drug therapy and the higher risk of lactic acidosis. Assess renal function more frequently in elderly patients [see Contraindications (4), Warnings and Precautions (5.1), and Clinical Pharmacology (12.3)].

8.6 Renal Impairment

A 26-week placebo-controlled study of 313 patients with Stage 3 Chronic Kidney Disease (eGFR ≥30 to less than 60 mL/min/1.73 m^2) treated with ertugliflozin did not have improvement in glycemic control.

In the VERTIS CV study, there were 1370 patients (25%) with an eGFR ≥90 mL/min/1.73 m^2, 2929 patients (53%) with an eGFR of ≥60 to less than 90 mL/min/1.73 m^2, 879 patients (16%) with an eGFR of ≥45 to less than 60 mL/min/1.73 m^2, and 299 patients (5%) with eGFR of 30 to <45 mL/min/1.73 m^2 treated with ertugliflozin. Similar effects on glycemic control at Week 18 were observed in patients treated with ertugliflozin in each eGFR subgroup and also in the overall patient population.

SEGLUROMET is contraindicated in patients with severe renal impairment (eGFR less than 30 mL/min/1.73 m^2), ESRD, or on dialysis [see Contraindications (4)].

No dosage adjustment is needed in patients with eGFR ≥45 mL/min/1.73 m^2.

Metformin is substantially excreted by the kidney, and the risk of metformin accumulation and lactic acidosis increases with the degree of renal impairment.

8.7 Hepatic Impairment

Use of metformin in patients with hepatic impairment has been associated with some cases of lactic acidosis. SEGLUROMET is not recommended in patients with hepatic impairment [see Warnings and Precautions (5.1)].

10 OVERDOSAGE

SEGLUROMET

In the event of an overdose with SEGLUROMET, contact the Poison Help line (1-800-222-1222) or a medical toxicologist for additional overdosage management recommendations. Employ the usual supportive measures as dictated by the patient's clinical status.

Ertugliflozin

Removal of ertugliflozin by hemodialysis has not been studied.

Metformin HCl

Overdose of metformin hydrochloride has occurred, including ingestion of amounts greater than 50 g (25 times the maximum recommended daily dose). Hypoglycemia was reported in approximately 10% of cases, but no causal association with metformin hydrochloride has been established. Lactic acidosis has been reported in approximately 32% of metformin overdose cases [see Warnings and Precautions (5.1)]. Metformin is dialyzable with a clearance of up to 170 mL/min under good hemodynamic conditions. Therefore, hemodialysis may be useful for removal of accumulated drug from patients in whom metformin overdosage is suspected.

11 DESCRIPTION

SEGLUROMET (ertugliflozin and metformin hydrochloride) tablet for oral use contains ertugliflozin L-pyroglutamic acid, a SGLT2 inhibitor, and metformin HCl, a member of the biguanide class.

Ertugliflozin

The chemical name of ertugliflozin L-pyroglutamic acid is (1S,2S,3S,4R,5S)-5-(4-chloro-3-(4-ethoxybenzyl)phenyl)-1-(hydroxymethyl)-6,8-dioxabicyclo[3.2.1]octane-2,3,4-triol, compound with (2S)-5-oxopyrrolidine-2-carboxylic acid. The molecular formula is C27H32ClNO10 and the molecular weight is 566.00.

The chemical structure is:

Ertugliflozin L-pyroglutamic acid is a white to off-white powder that is soluble in ethyl alcohol and acetone, slightly soluble in ethyl acetate and acetonitrile and very slightly soluble in water.

Metformin HCl

Metformin hydrochloride (N,N-dimethylimidodicarbonimidic diamide hydrochloride) is not chemically or pharmacologically related to any other classes of oral antihyperglycemic agents. The structural formula is as shown:

Metformin HCl is a white to off-white crystalline compound with a molecular formula of C4H11N5∙HCl and a molecular weight of 165.63. Metformin hydrochloride is freely soluble in water and is practically insoluble in acetone, ether and chloroform. The pKa of metformin is 12.4. The pH of a 1% aqueous solution of metformin hydrochloride is 6.68.

SEGLUROMET is available as film-coated tablets containing:

- 3.24 mg ertugliflozin L-pyroglutamic acid equivalent to 2.5 mg of ertugliflozin and 500 mg metformin HCl (SEGLUROMET 2.5/500)
- 3.24 mg ertugliflozin L-pyroglutamic acid equivalent to 2.5 mg of ertugliflozin and 1,000 mg metformin HCl (SEGLUROMET 2.5/1000)
- 9.71 mg ertugliflozin L-pyroglutamic acid equivalent to 7.5 mg of ertugliflozin and 500 mg metformin HCl (SEGLUROMET 7.5/500)
- 9.71 mg ertugliflozin L-pyroglutamic acid equivalent to 7.5 mg of ertugliflozin and 1,000 mg metformin HCl (SEGLUROMET 7.5/1000)

Inactive ingredients are povidone, microcrystalline cellulose, crospovidone, sodium lauryl sulfate, and magnesium stearate.

The film coating contains: hypromellose, hydroxypropyl cellulose, titanium dioxide, iron oxide red, and carnauba wax.

12 CLINICAL PHARMACOLOGY

12.1 Mechanism of Action

SEGLUROMET

SEGLUROMET combines two antihyperglycemic agents with complementary mechanisms of action to improve glycemic control in patients with type 2 diabetes mellitus: ertugliflozin, a SGLT2 inhibitor, and metformin hydrochloride, a member of the biguanide class.

Ertugliflozin

SGLT2 is the predominant transporter responsible for reabsorption of glucose from the glomerular filtrate back into the circulation. Ertugliflozin is an inhibitor of SGLT2. By inhibiting SGLT2, ertugliflozin reduces renal reabsorption of filtered glucose and lowers the renal threshold for glucose, and thereby increases urinary glucose excretion.

Metformin HCl

Metformin is an antihyperglycemic agent which improves glucose tolerance in patients with type 2 diabetes mellitus, lowering both basal and postprandial plasma glucose. Its pharmacologic mechanisms of action are different from other classes of oral antihyperglycemic agents. Metformin decreases hepatic glucose production, decreases intestinal absorption of glucose, and improves insulin sensitivity by increasing peripheral glucose uptake and utilization. Metformin does not produce hypoglycemia in either patients with type 2 diabetes mellitus or normal subjects (except in special circumstances) [see Warnings and Precautions (5.5)] and does not cause hyperinsulinemia. With metformin therapy, insulin secretion remains unchanged while fasting insulin levels and day-long plasma insulin response may actually decrease.

12.2 Pharmacodynamics

Ertugliflozin

Urinary Glucose Excretion and Urinary Volume

Dose-dependent increases in the amount of glucose excreted in urine were observed in healthy subjects and in patients with type 2 diabetes mellitus following single- and multiple-dose administration of ertugliflozin. Dose-response modeling indicates that ertugliflozin 5 mg and 15 mg result in near maximal urinary glucose excretion (UGE). Enhanced UGE is maintained after multiple-dose administration. UGE with ertugliflozin also results in increases in urinary volume.

Cardiac Electrophysiology

The effect of ertugliflozin on QTc interval was evaluated in a Phase 1 randomized, placebo- and positive-controlled 3-period crossover study in 42 healthy subjects. At 6.7 times the therapeutic exposures with maximum recommended dose, ertugliflozin does not prolong QTc to any clinically relevant extent.

12.3 Pharmacokinetics

General Introduction

Ertugliflozin

The pharmacokinetics of ertugliflozin are similar in healthy subjects and patients with type 2 diabetes mellitus. The steady state mean plasma AUC and Cmax were 398 ng∙hr/mL and 81.3 ng/mL, respectively, with 5 mg ertugliflozin once-daily treatment, and 1,193 ng∙hr/mL and 268 ng/mL, respectively, with 15 mg ertugliflozin once-daily treatment. Steady-state is reached after 4 to 6 days of once-daily dosing with ertugliflozin. Ertugliflozin does not exhibit time-dependent pharmacokinetics and accumulates in plasma up to 10-40% following multiple dosing.

Absorption

SEGLUROMET

The effects of a high-fat meal on the pharmacokinetics of ertugliflozin and metformin when administered as SEGLUROMET tablets are comparable to those reported for the individual tablets. Food had no meaningful effect on AUCinf of ertugliflozin and metformin, but reduced mean ertugliflozin Cmax by approximately 41% and metformin Cmax by approximately 29% compared to the fasted condition.

Ertugliflozin

Following single-dose oral administration of 5 mg and 15 mg of ertugliflozin, peak plasma concentrations of ertugliflozin occur at 1 hour postdose (median Tmax) under fasted conditions. Plasma Cmax and AUC of ertugliflozin increase in a dose-proportional manner following single doses from 0.5 mg (0.1 times the lowest recommended dose) to 300 mg (20 times the highest recommended dose) and following multiple doses from 1 mg (0.2 times the lowest recommended dose) to 100 mg (6.7 times the highest recommended dose). The absolute oral bioavailability of ertugliflozin following administration of a 15 mg dose is approximately 100%.

Effect of Food

Administration of ertugliflozin with a high-fat and high-calorie meal decreases ertugliflozin Cmax by 29% and prolongs Tmax by 1 hour, but does not alter AUC as compared with the fasted state. The observed effect of food on ertugliflozin pharmacokinetics is not considered clinically relevant, and ertugliflozin may be administered with or without food. In Phase 3 clinical trials, ertugliflozin was administered without regard to meals.

Metformin hydrochloride

The absolute bioavailability of a metformin HCl 500-mg tablet given under fasting conditions is approximately 50-60%. Studies using single oral doses of metformin hydrochloride tablets 500 mg to 1,500 mg, and 850 mg to 2,550 mg (approximately 1.3 times the maximum recommended daily dosage), indicate that there is a lack of dose proportionality with increasing doses, which is due to decreased absorption rather than an alternation in elimination. Food decreases the extent of and slightly delays the absorption of metformin, as shown by approximately a 40% lower mean peak plasma concentration (Cmax), a 25% lower area under the plasma concentration versus time curve (AUC), and a 35-minute prolongation of time to peak plasma concentration (Tmax) following administration of a single 850-mg tablet of metformin with food, compared to the same tablet strength administered fasting. The clinical relevance of these decreases is unknown.

Distribution

Ertugliflozin

The mean steady-state volume of distribution of ertugliflozin following an intravenous dose is 85.5 L. Plasma protein binding of ertugliflozin is 93.6% and is independent of ertugliflozin plasma concentrations. Plasma protein binding is not meaningfully altered in patients with renal or hepatic impairment. The blood-to-plasma concentration ratio of ertugliflozin is 0.66.

Metformin

The apparent volume of distribution (V/F) of metformin following single oral doses of metformin hydrochloride tablets 850 mg averaged 654 ± 358 L. Metformin is negligibly bound to plasma proteins, in contrast to sulfonylureas, which are more than 90% protein bound. Metformin partitions into erythrocytes, most likely as a function of time. At usual clinical doses and dosing schedules of metformin hydrochloride tablets, steady-state plasma concentrations of metformin are reached within 24-48 hours and are generally <1 mcg/mL. During controlled clinical trials of metformin, maximum metformin plasma levels did not exceed 5 mcg/mL, even at maximum doses.

Elimination

Metabolism

Ertugliflozin

Metabolism is the primary clearance mechanism for ertugliflozin. The major metabolic pathway for ertugliflozin is UGT1A9 and UGT2B7-mediated O-glucuronidation to two glucuronides that are pharmacologically inactive at clinically relevant concentrations. CYP-mediated (oxidative) metabolism of ertugliflozin is minimal (12%).

Metformin

Intravenous single-dose studies in normal subjects demonstrate that metformin is excreted unchanged in the urine and does not undergo hepatic metabolism (no metabolites have been identified in humans) nor biliary excretion.

Excretion

Ertugliflozin

The mean systemic plasma clearance following an intravenous 100 µg dose was 11.2 L/hr. The mean elimination half-life in type 2 diabetic patients with normal renal function was estimated to be 16.6 hours based on the population pharmacokinetic analysis. Following administration of an oral [^14C]-ertugliflozin solution to healthy subjects, approximately 40.9% and 50.2% of the drug-related radioactivity was eliminated in feces and urine, respectively. Only 1.5% of the administered dose was excreted as unchanged ertugliflozin in urine and 33.8% as unchanged ertugliflozin in feces, which is likely due to biliary excretion of glucuronide metabolites and subsequent hydrolysis to parent.

Metformin

Renal clearance is approximately 3.5 times greater than creatinine clearance, which indicates that tubular secretion is the major route of metformin elimination. Following oral administration, approximately 90% of the absorbed drug is eliminated via the renal route within the first 24 hours, with a plasma elimination half-life of approximately 6.2 hours. In blood, the elimination half-life is approximately 17.6 hours, suggesting that the erythrocyte mass may be a compartment of distribution.

Specific Populations

Patients with Renal Impairment

SEGLUROMET

Studies characterizing the pharmacokinetics of ertugliflozin and metformin after administration of SEGLUROMET in renally impaired patients have not been performed [see Dosage and Administration (2.2)].

Ertugliflozin

In a clinical pharmacology study in patients with type 2 diabetes mellitus and mild, moderate, or severe renal impairment (as determined by eGFR), following a single-dose administration of 15 mg ertugliflozin, the mean increases in AUC of ertugliflozin were 1.6-, 1.7-, and 1.6-fold, respectively, for mild, moderate, and severe renally-impaired patients compared to subjects with normal renal function. These increases in ertugliflozin AUC are not considered clinically meaningful. The 24-hour urinary glucose excretion declined with increasing severity of renal impairment [see Warnings and Precautions (5.2) and Use in Specific Populations (8.6)]. The plasma protein binding of ertugliflozin was unaffected in patients with renal impairment.

Metformin

In patients with decreased renal function, the plasma and blood half-life of metformin is prolonged and the renal clearance is decreased [see Contraindications (4) and Warnings and Precautions (5.1)].

Patients with Hepatic Impairment

Ertugliflozin

Moderate hepatic impairment (based on the Child-Pugh classification) did not result in an increase in exposure of ertugliflozin. The AUC of ertugliflozin decreased by approximately 13%, and Cmax decreased by approximately 21% compared to subjects with normal hepatic function. This decrease in ertugliflozin exposure is not considered clinically meaningful. There is no clinical experience in patients with Child-Pugh class C (severe) hepatic impairment. The plasma protein binding of ertugliflozin was unaffected in patients with moderate hepatic impairment [see Use in Specific Populations (8.7)].

Metformin

No pharmacokinetic studies of metformin have been conducted in patients with hepatic impairment [see Use in Specific Populations (8.7)].

Effects of Age, Body Weight, Gender, and Race

Ertugliflozin

Based on a population pharmacokinetic analysis, age, body weight, gender, and race do not have a clinically meaningful effect on the pharmacokinetics of ertugliflozin.

Metformin

Limited data from controlled pharmacokinetic studies of metformin in healthy elderly subjects suggest that total plasma clearance of metformin is decreased, the half-life is prolonged, and Cmax is increased, compared to healthy young subjects. From these data, it appears that the change in metformin pharmacokinetics with aging is primarily accounted for by a change in renal function.

Metformin pharmacokinetic parameters did not differ significantly between normal subjects and patients with type 2 diabetes mellitus when analyzed according to gender. Similarly, in controlled clinical studies in patients with type 2 diabetes mellitus, the antihyperglycemic effect of metformin was comparable in males and females.

No studies of metformin pharmacokinetic parameters according to race have been performed. In controlled clinical studies of metformin in patients with type 2 diabetes mellitus, the antihyperglycemic effect was comparable in Whites (n=249), Blacks (n=51), and Hispanics (n=24).

Drug Interaction Studies

SEGLUROMET

Coadministration of single dose of ertugliflozin (15 mg) and metformin (1,000 mg) did not meaningfully alter the pharmacokinetics of either ertugliflozin or metformin in healthy subjects.

Pharmacokinetic drug interaction studies with SEGLUROMET have not been performed; however, such studies have been conducted with ertugliflozin and metformin, the individual components of SEGLUROMET.

Ertugliflozin

In Vitro Assessment of Drug Interactions

In in vitro studies, ertugliflozin and ertugliflozin glucuronides did not inhibit CYP450 isoenzymes (CYPs) 1A2, 2C9, 2C19, 2C8, 2B6, 2D6, or 3A4, and did not induce CYPs 1A2, 2B6, or 3A4. Ertugliflozin was not a time-dependent inhibitor of CYP3A in vitro. Ertugliflozin did not inhibit UGT1A6, 1A9, or 2B7 in vitro and was a weak inhibitor (IC50 >39 µM) of UGT1A1 and 1A4. Ertugliflozin glucuronides did not inhibit UGT1A1, 1A4, 1A6, 1A9, or 2B7 in vitro. Overall, ertugliflozin is unlikely to affect the pharmacokinetics of drugs eliminated by these enzymes. Ertugliflozin is a substrate of P-glycoprotein (P-gp) and breast cancer resistance protein (BCRP) transporters and is not a substrate of organic anion transporters (OAT1, OAT3), organic cation transporters (OCT1, OCT2), or organic anion transporting polypeptides (OATP1B1, OATP1B3). Ertugliflozin or ertugliflozin glucuronides do not meaningfully inhibit P-gp, OCT2, OAT1, or OAT3 transporters, or transporting polypeptides OATP1B1 and OATP1B3, at clinically relevant concentrations. Overall, ertugliflozin is unlikely to affect the pharmacokinetics of concurrently administered medications that are substrates of these transporters.

In Vivo Assessment of Drug Interactions

No dose adjustment of SEGLUROMET is recommended when coadministered with commonly prescribed medicinal products. Ertugliflozin pharmacokinetics were similar with and without coadministration of metformin, glimepiride, sitagliptin, and simvastatin in healthy subjects (see Figure 1). Coadministration of ertugliflozin with multiple doses of 600 mg once-daily rifampin (an inducer of UGT and CYP enzymes) resulted in approximately 39% and 15% mean reductions in ertugliflozin AUC and Cmax, respectively, relative to ertugliflozin administered alone. These changes in exposure are not considered clinically relevant. Ertugliflozin had no clinically relevant effect on the pharmacokinetics of metformin, glimepiride, sitagliptin, and simvastatin when coadministered in healthy subjects (see Figure 2). Physiologically-based PK (PBPK) modeling suggests that coadministration of mefenamic acid (UGT inhibitor) may increase the AUC and Cmax of ertugliflozin by 1.51- and 1.19-fold, respectively. These predicted changes in exposure are not considered clinically relevant.

Figure 1: Effects of Other Drugs on the Pharmacokinetics of Ertugliflozin

Figure 2: Effects of Ertugliflozin on the Pharmacokinetics of Other Drugs

Metformin hydrochloride

Table 4: Effect of Metformin HCl on Systemic Exposure of Coadministered Drugs
Coadministered Drug | Dose of Coadministered Drug [All doses administered as single dose unless otherwise specified.] | Dose of Metformin HCl | Geometric Mean Ratio (ratio with/without metformin) No Effect = 1.00
 |  |  |  | AUC [AUC is reported as AUC0-∞ unless otherwise specified.] | Cmax
No dosing adjustments required for the following:
Cimetidine | 400 mg | 850 mg | Cimetidine | 0.95 [AUC0-24hr.] | 1.01
Glyburide | 5 mg | 500 mg [Metformin HCl extended-release tablets 500 mg.] | Glyburide | 0.78 [Ratio of arithmetic means, p value of difference <0.05.] | 0.63
Furosemide | 40 mg | 850 mg | Furosemide | 0.87 | 0.69
Nifedipine | 10 mg | 850 mg | Nifedipine | 1.10 | 1.08
Propranolol | 40 mg | 850 mg | Propranolol | 1.01 | 0.94
Ibuprofen | 400 mg | 850 mg | Ibuprofen | 0.97 [Ratio of arithmetic means.] | 1.01

Table 5: Effect of Coadministered Drugs on Systemic Exposure of Metformin HCl
Coadministered Drug | Dose of Coadministered Drug [All doses administered as single dose unless otherwise specified.] | Dose of Metformin HCl | Geometric Mean Ratio (ratio with/without coadministered drug) No Effect = 1.00
 |  |  |  | AUC [AUC is reported as AUC0-∞ unless otherwise specified.] | Cmax
No dosing adjustments required for the following:
Glyburide | 5 mg | 500 mg [Metformin hydrochloride extended-release tablets 500 mg.] | Metformin | 0.98 [Ratio of arithmetic means.] | 0.99
Furosemide | 40 mg | 850 mg | Metformin | 1.09 | 1.22
Nifedipine | 10 mg | 850 mg | Metformin | 1.16 | 1.21
Propranolol | 40 mg | 850 mg | Metformin | 0.90 | 0.94
Ibuprofen | 400 mg | 850 mg | Metformin | 1.05 | 1.07
Drugs that are eliminated by renal tubular secretion may increase the accumulation of metformin [see Warnings and Precautions (5.1) and Drug Interactions (7.2)].
Cimetidine | 400 mg | 850 mg | Metformin | 1.40 | 1.61
Carbonic anhydrase inhibitors may cause metabolic acidosis [see Warnings and Precautions (5.1) and Drug Interactions (7.2)].
Topiramate | 100 mg [Steady-state 100 mg topiramate every 12 hr + metformin 500 mg every 12 hr AUC = AUC0-12hr.] | 500 mg | Metformin | 1.25 | 1.17

13 NONCLINICAL TOXICOLOGY

13.1 Carcinogenesis, Mutagenesis, Impairment of Fertility

Carcinogenesis

Ertugliflozin

Carcinogenicity was evaluated in CD-1 mice and Sprague-Dawley rats. In the mouse study, ertugliflozin was administered by oral gavage at doses of 5, 15, and 40 mg/kg/day for up to 97 weeks in males and 102 weeks in females. There were no ertugliflozin-related neoplastic findings at doses up to 40 mg/kg/day (approximately 50 times human exposure at the maximum recommended human dose [MRHD] of 15 mg/day based on AUC). In the rat study, ertugliflozin was administered by oral gavage at doses of 1.5, 5, and 15 mg/kg/day for up to 92 weeks in females and 104 weeks in males. Ertugliflozin-related neoplastic findings included an increased incidence of adrenal medullary pheochromocytoma (PCC) in male rats at 15 mg/kg/day. Although the molecular mechanism remains unknown, this finding may be related to carbohydrate malabsorption leading to altered calcium homeostasis, which has been associated with PCC development in rats and has unclear relevancy to human risk. The no-observed-effect level (NOEL) for neoplasia was 5 mg/kg/day (approximately 16 times human exposure at the MRHD of 15 mg/day, based on AUC).

Metformin HCl

Long-term carcinogenicity studies have been performed in rats (dosing duration of 104 weeks) and mice (dosing duration of 91 weeks) at doses up to and including 900 mg/kg/day and 1,500 mg/kg/day, respectively. These doses are both approximately four times the maximum recommended human daily dose of 2,000 mg based on body surface area comparisons. No evidence of carcinogenicity with metformin was found in either male or female mice. Similarly, there was no tumorigenic potential observed with metformin in male rats. There was, however, an increased incidence of benign stromal uterine polyps in female rats treated with 900 mg/kg/day.

Mutagenesis

Ertugliflozin

Ertugliflozin was not mutagenic or clastogenic with or without metabolic activation in the microbial reverse mutation, in vitro cytogenetic (human lymphocytes), and in vivo rat micronucleus assays.

Metformin

There was no evidence of a mutagenic potential of metformin in the following in vitro tests: Ames test (S. typhimurium), gene mutation test (mouse lymphoma cells), or chromosomal aberrations test (human lymphocytes). Results in the in vivo mouse micronucleus test were also negative.

Impairment of Fertility

Ertugliflozin

In the rat fertility and embryonic development study, male and female rats were administered ertugliflozin at 5, 25, and 250 mg/kg/day. No effects on fertility were observed at 250 mg/kg/day (approximately 480 and 570 times male and female human exposures, respectively, at the MRHD of 15 mg/day based on AUC comparison).

Metformin HCl

Fertility of male or female rats was unaffected by metformin when administered at doses as high as 600 mg/kg/day, which is approximately three times the maximum recommended human daily dose based on body surface area comparisons.

14 CLINICAL STUDIES

14.1 Glycemic Control Trials in Patients with Type 2 Diabetes Mellitus

The efficacy and safety of ertugliflozin in combination with metformin HCl have been studied in 4 multicenter, randomized, double-blind, placebo- and active comparator-controlled, clinical studies involving 3,643 patients with type 2 diabetes mellitus. These studies included White, Hispanic or Latino, Black or African American, Asian, and other racial and ethnic groups, and patients with an age range of 21 to 86 years.

In VERTIS CV, ertugliflozin has been studied as add on to insulin (with or without metformin HCl) and as add on to metformin HCl plus a sulfonylurea in substudies.

In patients with type 2 diabetes mellitus, treatment with ertugliflozin in combination with metformin HCl reduced hemoglobin A1c (HbA1c) compared to placebo.

In patients with type 2 diabetes mellitus treated with ertugliflozin in combination with metformin HCl, the reduction in HbA1c was generally similar across subgroups defined by age, sex, race, geographic region, baseline body mass index (BMI), and duration of type 2 diabetes mellitus.

Ertugliflozin as Add-on Combination Therapy with Metformin HCl

A total of 621 patients with type 2 diabetes mellitus inadequately controlled (HbA1c between 7% and 10.5%) on metformin HCl monotherapy (≥1,500 mg/day for ≥8 weeks) participated in a randomized, double-blind, multi-center, 26-week, placebo-controlled study (NCT02033889) to evaluate the efficacy and safety of ertugliflozin in combination with metformin HCl. Patients entered a 2-week, single-blind, placebo run-in, and were randomized to placebo, ertugliflozin 5 mg, or ertugliflozin 15 mg administered orally once daily in addition to continuation of background metformin HCl therapy.

At Week 26, statistically significant reductions in HbA1c were observed in the ertugliflozin 5 mg and 15 mg groups compared to placebo. Ertugliflozin also resulted in a greater proportion of patients achieving an HbA1c <7% compared to placebo (see Table 6 and Figure 3).

Table 6: Results at Week 26 from a Placebo-Controlled Study for Ertugliflozin Used in Combination with Metformin HCl in Patients with Type 2 Diabetes Mellitus [N includes all randomized and treated patients with a baseline measurement of the outcome variable. At Week 26, the primary HbA1c endpoint was missing for 12%, 6%, and 9% of patients, and during the trial, rescue medication was initiated by 18%, 3%, and 1% of patients randomized to placebo, ertugliflozin 5 mg, and ertugliflozin 15 mg, respectively. Missing Week 26 measurements were imputed using multiple imputation with a mean equal to the baseline value of the patient. Results include measurements collected after initiation of rescue medication. For those patients who did not receive rescue medication and had values measured at 26 weeks, the mean changes from baseline for HbA1c were -0.2%, -0.7%, and -1.0% for placebo, ertugliflozin 5 mg, and ertugliflozin 15 mg, respectively.]
 | Placebo | Ertugliflozin 5 mg | Ertugliflozin 15 mg
HbA1c (%) | N = 207 | N = 205 | N = 201
Baseline (mean) | 8.2 | 8.1 | 8.1
Change from baseline (LS mean [Intent-to-treat analysis using ANCOVA adjusted for baseline value, prior antihyperglycemic medication, menopausal status and baseline eGFR.]) | -0.2 | -0.7 | -0.9
Difference from placebo (LS mean, 95% CI) |  | -0.5 [p<0.001 compared to placebo.] (-0.7, -0.4) | -0.7 (-0.9, -0.5)
Patients [N (%)] with HbA1c <7% | 38 (18.4) | 74 (36.3) | 87 (43.3)
FPG (mg/dL) | N = 202 | N = 199 | N = 201
Baseline (mean) | 169.1 | 168.1 | 167.9
Change from baseline (LS mean) | -8.7 | -30.3 | -40.9
Difference from placebo (LS mean, 95% CI) |  | -21.6 (-27.8, -15.5) | -32.3 (-38.5, -26.0)

The mean baseline body weight was 84.5 kg, 84.9 kg, and 85.3 kg in the placebo, ertugliflozin 5 mg, and ertugliflozin 15 mg groups, respectively. The mean changes from baseline to Week 26 were -1.4 kg, -3.2 kg, and -3.0 kg in the placebo, ertugliflozin 5 mg, and ertugliflozin 15 mg groups, respectively. The difference from placebo (95% CI) for ertugliflozin 5 mg was -1.8 kg (-2.4, -1.2) and for ertugliflozin 15 mg was -1.7 kg (-2.2, -1.1).

The mean baseline systolic blood pressure was 129.3 mmHg, 130.5 mmHg, and 130.2 mmHg in the placebo, ertugliflozin 5 mg, and ertugliflozin 15 mg groups, respectively. The mean changes from baseline to Week 26 were -1.8 mmHg, -5.1 mmHg, and -5.7 mmHg in the placebo, ertugliflozin 5 mg, and ertugliflozin 15 mg groups, respectively. The difference from placebo (95% CI) for ertugliflozin 5 mg was -3.3 mmHg (-5.6, -1.1) and for ertugliflozin 15 mg was -3.8 mmHg (-6.1, -1.5).

Figure 3: HbA1c (%) Change over Time in a 26-Week Placebo-Controlled Study for Ertugliflozin Used in Combination with Metformin HCl in Patients with Type 2 Diabetes Mellitus [Data to the left of the vertical line are observed means (non-model-based) excluding values occurring post glycemic rescue. Data to the right of the vertical line represent the final Week 26 data, including all values regardless of use of glycemic rescue medication and use of study drug, with missing Week 26 values imputed using multiple imputation (26-MI) with a mean equal to the baseline value of the patient (see Table 6).]

In Combination with Sitagliptin versus Ertugliflozin Alone and Sitagliptin Alone, as Add-on to Metformin HCl

A total of 1,233 patients with type 2 diabetes mellitus with inadequate glycemic control (HbA1c between 7.5% and 11%) on metformin HCl monotherapy (≥1,500 mg/day for ≥8 weeks) participated in a randomized, double-blind, 26-week, active controlled study (NCT02099110) to evaluate the efficacy and safety of ertugliflozin 5 mg or 15 mg administered orally in combination with sitagliptin 100 mg compared to the individual components. Patients were randomized to one of five treatment arms: ertugliflozin 5 mg, ertugliflozin 15 mg, sitagliptin 100 mg, ertugliflozin 5 mg + sitagliptin 100 mg, or ertugliflozin 15 mg + sitagliptin 100 mg.

At Week 26, ertugliflozin 5 mg or 15 mg + sitagliptin 100 mg provided statistically significantly greater reductions in HbA1c compared to ertugliflozin (5 mg or 15 mg) alone or sitagliptin 100 mg alone. The mean change from baseline in HbA1c was -1.4% for ertugliflozin 5 mg or 15 mg + sitagliptin 100 mg versus -1.0%, for ertugliflozin 5 mg, ertugliflozin 15 mg, or sitagliptin 100 mg, respectively. More patients receiving ertugliflozin 5 mg or 15 mg + sitagliptin 100 mg achieved an HbA1c <7% (53.3% and 50.9%, for ertugliflozin 5 mg or 15 mg, respectively, + sitagliptin 100 mg) compared to the individual components (29.3%, 33.7%, and 38.5% for ertugliflozin 5 mg, ertugliflozin 15 mg, or sitagliptin 100 mg, respectively).

Ertugliflozin as Add-on Combination Therapy with Metformin HCl and Sitagliptin

A total of 463 patients with type 2 diabetes mellitus inadequately controlled (HbA1c between 7% and 10.5%) on metformin HCl (≥1,500 mg/day for ≥8 weeks) and sitagliptin 100 mg orally once daily participated in a randomized, double-blind, multi-center, 26-week, placebo-controlled study (NCT02036515) to evaluate the efficacy and safety of ertugliflozin. Patients entered a 2-week, single-blind, placebo run-in period and were randomized to placebo, ertugliflozin 5 mg, or ertugliflozin 15 mg.

At Week 26, treatment with ertugliflozin at 5 mg or 15 mg daily provided statistically significant reductions in HbA1c. Ertugliflozin also resulted in a higher proportion of patients achieving an HbA1c <7% compared to placebo (see Table 7).

Table 7: Results at Week 26 from an Add-on Study of Ertugliflozin in Combination with Metformin HCl and Sitagliptin in Patients with Type 2 Diabetes Mellitus [N includes all randomized and treated patients with a baseline measurement of the outcome variable. At Week 26, the primary HbA1c endpoint was missing for 10%, 11%, and 7% of patients and during the trial, rescue medication was initiated by 16%, 1%, and 2% of patients randomized to placebo, ertugliflozin 5 mg, and ertugliflozin 15 mg, respectively. Missing Week 26 measurements were imputed using multiple imputation with a mean equal to the baseline value of the patient. Results include measurements collected after initiation of rescue medication. For those patients who did not receive rescue medication and had values measured at 26 weeks, the mean changes from baseline for HbA1c were -0.2%, -0.8%, and -0.9% for placebo, ertugliflozin 5 mg, and ertugliflozin 15 mg, respectively.]
 | Placebo | Ertugliflozin 5 mg | Ertugliflozin 15 mg
HbA1c (%) | N = 152 | N = 155 | N = 152
Baseline (mean) | 8.0 | 8.1 | 8.0
Change from baseline (LS mean [Intent-to-treat analysis using ANCOVA adjusted for baseline value, prior antihyperglycemic medication and baseline eGFR.]) | -0.2 | -0.7 | -0.8
Difference from placebo (LS mean, 95% CI) |  | -0.5 [p<0.001 compared to placebo.] (-0.7, -0.3) | -0.6 (-0.8, -0.4)
Patients [N (%)] with HbA1c <7% | 31 (20.2) | 54 (34.6) | 64 (42.3)
FPG (mg/dL) | N = 152 | N = 156 | N = 152
Baseline (mean) | 169.6 | 167.7 | 171.7
Change from baseline (LS mean) | -6.5 | -25.7 | -32.1
Difference from placebo (LS mean, 95% CI) |  | -19.2 (-26.8, -11.6) | -25.6 (-33.2, -18.0)

The mean baseline body weight was 86.5 kg, 87.6 kg, and 86.6 kg in the placebo, ertugliflozin 5 mg, and ertugliflozin 15 mg groups, respectively. The mean changes from baseline to Week 26 were -1.0 kg, -3.0 kg, and -2.8 kg in the placebo, ertugliflozin 5 mg, and ertugliflozin 15 mg groups, respectively. The difference from placebo (95% CI) for ertugliflozin 5 mg was -1.9 kg (-2.6, -1.3) and for ertugliflozin 15 mg was -1.8 kg (-2.4, -1.2).

The mean baseline systolic blood pressure was 130.2 mmHg, 132.1 mmHg, and 131.6 mmHg in the placebo, ertugliflozin 5 mg, and ertugliflozin 15 mg groups, respectively. The mean changes from baseline to Week 26 were -0.2 mmHg, -3.8 mmHg, and -4.5 mmHg in the placebo, ertugliflozin 5 mg, and ertugliflozin 15 mg groups, respectively. The difference from placebo (95% CI) for ertugliflozin 5 mg was -3.7 mmHg (-6.1, -1.2) and for ertugliflozin 15 mg was -4.3 mmHg (-6.7, -1.9).

Active Controlled Study of Ertugliflozin Versus Glimepiride as Add-on Combination Therapy with Metformin HCl

A total of 1,326 patients with type 2 diabetes mellitus inadequately controlled (HbA1c between 7% and 9%) on metformin HCl monotherapy participated in a randomized, double-blind, multi-center, 52-week, active comparator-controlled study (NCT01999218) to evaluate the efficacy and safety of ertugliflozin in combination with metformin HCl. These patients, who were receiving metformin HCl monotherapy (≥1,500 mg/day for ≥8 weeks), entered a 2-week, single-blind, placebo run-in period and were randomized to glimepiride, ertugliflozin 5 mg, or ertugliflozin 15 mg, administered orally once daily in addition to continuation of background metformin HCl therapy. Glimepiride was initiated at 1 mg/day and titrated up to a maximum dose of 6 or 8 mg/day (depending on maximum approved dose in each country) or a maximum tolerated dose or down-titrated to avoid or manage hypoglycemia. The mean daily dose of glimepiride was 3.0 mg.

Ertugliflozin 15 mg was non-inferior to glimepiride after 52 weeks of treatment. (See Table 8.)

Table 8: Results at Week 52 from an Active-Controlled Study Comparing Ertugliflozin to Glimepiride as Add-on Therapy in Patients with Type 2 Diabetes Mellitus Inadequately Controlled on Metformin HCl [N includes all randomized and treated patients with a baseline measurement of the outcome variable. At Week 52, the primary HbA1c endpoint was missing for 15%, 20%, and 16% of patients and during the trial, rescue medication was initiated by 3%, 6%, and 4% of patients randomized to glimepiride, ertugliflozin 5 mg, and ertugliflozin 15 mg, respectively. Missing Week 52 measurements were imputed using multiple imputation with a mean equal to the baseline value of the patient. Results include measurements collected after initiation of rescue medication. For those patients who did not receive rescue medication and had values measured at 52 weeks, the mean changes from baseline for HbA1c were -0.8%, -0.6%, and -0.7% for glimepiride, ertugliflozin 5 mg, and ertugliflozin 15 mg, respectively.]
 | Glimepiride | Ertugliflozin 5 mg | Ertugliflozin 15 mg
HbA1c (%) | N = 437 | N = 447 | N = 440
Baseline (mean) | 7.8 | 7.8 | 7.8
Change from baseline (LS mean [Intent-to-treat analysis using ANCOVA adjusted for baseline value, prior antihyperglycemic medication and baseline eGFR.]) | -0.6 | -0.5 | -0.5
Difference from glimepiride (LS mean, 95% CI) |  | 0.2 [Non-inferiority is declared when the upper bound of the two-sided 95% confidence interval (CI) for the mean difference is less than 0.3%.] (0.0, 0.3) | 0.1 (-0.0, 0.2)
Patients [N (%)] with HbA1c <7% | 208 (47.7) | 177 (39.5) | 186 (42.2)

The mean baseline body weight was 86.8 kg, 87.9 kg, and 85.6 kg in the glimepiride, ertugliflozin 5 mg, and ertugliflozin 15 mg groups, respectively. The mean changes from baseline to Week 52 were 0.6 kg, -2.6 kg, and -3.0 kg in the glimepiride, ertugliflozin 5 mg, and ertugliflozin 15 mg groups, respectively. The difference from glimepiride (95% CI) for ertugliflozin 5 mg was -3.2 kg (-3.7, -2.7) and for ertugliflozin 15 mg was -3.6 kg (-4.1, -3.1).

Ertugliflozin as Add-on Combination Therapy with Insulin (With or Without Metformin HCl)

In an 18-week randomized, double-blind, multi-center, placebo-controlled, glycemic sub-study of VERTIS CV (NCT01986881, study details see 14.2), a total of 1,065 patients with type 2 diabetes mellitus and established atherosclerotic cardiovascular disease with inadequate glycemic control (HbA1c between 7% and 10.5%) on background therapy of insulin ≥20 units/day (59% also on metformin HCl ≥1,500 mg/day) were randomized to placebo, ertugliflozin 5 mg or ertugliflozin 15 mg oral once daily treatment.

At Week 18, treatment with ertugliflozin at 5 mg or 15 mg daily provided statistically significant reductions in HbA1c compared to placebo (see Table 9).

Table 9: Results at Week 18 from an Add-on Study of Ertugliflozin in Combination with Insulin (with or without Metformin HCl) in Patients with Type 2 Diabetes Mellitus [N includes all randomized and treated patients with a baseline measurement of the outcome variable. At Week 18, the primary HbA1c endpoint was missing for 10%, 9%, and 12% of patients and during the trial, rescue medication was initiated by 12%, 7%, and 6% of patients randomized to placebo, ertugliflozin 5 mg, and ertugliflozin 15 mg, respectively. Results include measurements collected after initiation of rescue medication. Prior to Week 18, background antidiabetic medication was held stable. Missing Week 18 measurements were imputed using multiple imputation with a mean equal to the baseline value of the patient (Return to Baseline analysis).]
 | Placebo | Ertugliflozin 5 mg | Ertugliflozin 15 mg
HbA1c (%) | N = 346 | N = 346 | N = 367
Baseline (mean) | 8.4 | 8.4 | 8.4
Change from baseline (LS mean [Intent-to-treat analysis using ANCOVA adjusted for baseline value, insulin stratum, and baseline eGFR.] , SE) | -0.2 (0.05) | -0.7 (0.05) | -0.7 (0.05)
Difference from placebo (LS mean, 95% CI) |  | -0.5 [p<0.001 compared to placebo.] (-0.6, -0.4) | -0.5 (-0.7, -0.4)
Patients [N (%)] with HbA1c <7% [Missing values imputed as not meeting the <7% criterion.] | 37 (10.7) | 79 (22.8) | 81 (22.1)
FPG (mg/dL) | N = 343 | N = 346 | N = 368
Baseline (mean) | 167.4 | 173.8 | 175.4
Change from baseline (LS mean, SE) | -6.3 (2.91) | -25.6 (2.90) | -29.8 (2.86)
Difference from placebo (LS mean, 95% CI) |  | -19.2 (-26.8, -11.6) | -23.4 (-30.9, -16.0)
SE: standard error.

The mean baseline body weights were 93.3 kg, 93.8 kg, and 92.1 kg in the placebo, ertugliflozin 5 mg, and ertugliflozin 15 mg groups, respectively. The mean changes from baseline to Week 18 were -0.2 kg, - 1.6 kg, and -1.9 kg in the placebo, ertugliflozin 5 mg, and ertugliflozin 15 mg groups, respectively. The differences from placebo (95% CI) for ertugliflozin 5 mg were - 1.4 kg (- 1.9, - 0.9) and for ertugliflozin 15 mg was -1.6 kg (-2.1, -1.1).

The mean baseline systolic blood pressures were 134.0 mmHg, 135.6 mmHg, and 133.7 mmHg in the placebo, ertugliflozin 5 mg, and ertugliflozin 15 mg groups, respectively. The mean changes from baseline to Week 18 were 0.7 mmHg, -2.2 mmHg, and -1.7 mmHg in the placebo, ertugliflozin 5 mg, and ertugliflozin 15 mg groups, respectively. The differences from placebo (95% CI) for ertugliflozin 5 mg was – 2.9 mmHg (-4.9, -1.0) and for ertugliflozin 15 mg were -2.5 mmHg (- 4.4, - 0.5).

Add-on Combination Therapy with Metformin HCl and Sulfonylurea

In an 18-week randomized, double-blind, multi-center, placebo-controlled, glycemic sub-study of VERTIS CV (NCT01986881, study details see 14.2), a total of 330 patients with type 2 diabetes mellitus and established atherosclerotic cardiovascular disease with inadequate glycemic control (HbA1c between 7% and 10.5%) with background therapy of metformin HCl ≥1,500 mg/day and a sulfonylurea (SU) were randomized to placebo, ertugliflozin 5 mg or ertugliflozin 15 mg oral once daily treatment.

At Week 18, treatment with ertugliflozin at 5 mg or 15 mg daily provided statistically significant reductions in HbA1c compared to placebo (see Table 10).

Table 10: Results at Week 18 from an Add-on Study of Ertugliflozin in Combination with Metformin HCl and a SU in Patients with Type 2 Diabetes Mellitus [N includes all randomized and treated patients with a baseline measurement of the outcome variable. At Week 18, the primary HbA1c endpoint was missing for 9%, 8%, and 6% of patients and during the trial, rescue medication was initiated by 10%, 7%, and 3% of patients randomized to placebo, ertugliflozin 5 mg, and ertugliflozin 15 mg, respectively. Results include measurements collected after initiation of rescue medication. Missing Week 18 measurements were imputed using multiple imputation with a mean equal to the baseline value of the patient (Return to Baseline analysis).]
 | Placebo | Ertugliflozin 5 mg | Ertugliflozin 15 mg
HbA1c (%) | N = 116 | N = 99 | N = 113
Baseline (mean) | 8.3 | 8.4 | 8.3
Change from baseline (LS mean [Intent-to-treat analysis using ANCOVA adjusted for baseline value and baseline eGFR.] , SE) | -0.3 (0.08) | -0.8 (0.09) | -0.9 (0.08)
Difference from placebo (LS mean, 95% CI) |  | -0.6 [p<0.001 compared to placebo.] (-0.8, -0.3) | -0.7 (-0.9, -0.4)
Patients [N (%)] with HbA1c <7% [Missing values imputed as not meeting the <7% criterion.] | 17 (14.7) | 39 (39.4) | 38 (33.6)
FPG (mg/dL) | N = 117 | N = 99 | N = 113
Baseline (mean) | 177.3 | 183.5 | 174.0
Change from baseline (LS mean, SE) | -3.5 (3.65) | -31.3 (3.87) | -33.0 (3.67)
Difference from placebo (LS mean, 95% CI) |  | -27.9 (-37.8, -17.9) | -29.5 (-39.0, -19.9)
SE: standard error

The mean baseline body weights were 90.5 kg, 92.1 kg, and 92.9 kg in the placebo, ertugliflozin 5 mg, and ertugliflozin 15 mg groups, respectively. The mean changes from baseline to Week 18 were - 0.6 kg, -2.0 kg, and - 2.2 kg in the placebo, ertugliflozin 5 mg, and ertugliflozin 15 mg groups, respectively. The differences from placebo (95% CI) for ertugliflozin 5 mg were - 1.4 kg (- 2.2, - 0.7) and for ertugliflozin 15 mg was - 1.6 kg (- 2.3, - 0.9).

14.2 Ertugliflozin Cardiovascular Outcomes in Patients with Type 2 Diabetes and Established Cardiovascular Disease

The effect of ertugliflozin on cardiovascular risk in adult patients with type 2 diabetes and established atherosclerotic cardiovascular disease was evaluated in the VERTIS CV study (NCT 01986881), a multicenter, multi-national, randomized, double-blind, placebo-controlled, event-driven trial. The study compared the risk of experiencing a major adverse cardiovascular event (MACE) between ertugliflozin and placebo when these were added to and used concomitantly with standard of care treatments for diabetes and atherosclerotic cardiovascular disease.

A total of 8,246 patients were randomized to placebo (N=2,747), oral once daily ertugliflozin 5 mg (N=2,752), or oral once daily ertugliflozin 15 mg (N=2,747) and followed for a median of 3 years. Approximately 88% of the study population was White, 6% Asian, and 3% Black or African American. The mean age was 64 years and approximately 70% were male.

All patients in the study had inadequately controlled type 2 diabetes mellitus at baseline (HbA1c greater than or equal to 7%). The mean duration of type 2 diabetes mellitus was 13 years, the mean HbA1c at baseline was 8.2% and the mean eGFR was 76 mL/min/1.73 m^2. At baseline, patients were treated with one (32%) or more (67%) antidiabetic medications including biguanides (metformin HCl) (76%), insulin (47%), sulfonylureas (41%), DPP-4 inhibitors (11%) and GLP-1 receptor agonists (3%).

Almost all patients (99%) had established atherosclerotic cardiovascular disease at baseline including: a documented history of coronary artery disease (76%), cerebrovascular disease (23%) or peripheral artery disease (19%). Approximately 24% patients had a history of heart failure (HF). At baseline, the mean systolic blood pressure was 133 mmHg, the mean diastolic blood pressure was 77 mmHg, the mean LDL was 89 mg/dL, and the mean HDL was 44 mg/dL. At baseline, approximately 81% of patients were treated with renin angiotensin system inhibitors, 69% with beta-blockers, 43% with diuretics, 82% with statins, 4% ezetimibe, and 89% with antiplatelet agents.

The primary endpoint in VERTIS CV was the time to first occurrence of a Major Adverse Cardiac Event (MACE). A major adverse cardiovascular event was defined as occurrence of either a cardiovascular death or a nonfatal myocardial infarction (MI) or a nonfatal stroke. The statistical analysis plan pre-specified that the 5 and 15 mg doses would be combined for the analysis. A Cox proportional hazards model was used to test for non-inferiority against the pre-specified risk margin of 1.3 for the hazard ratio of MACE. Type-1 error was controlled across multiple tests using a hierarchical testing strategy.

The incidence rate of MACE was similar between the ertugliflozin-treated and placebo-treated patients. The estimated hazard ratio of MACE associated with ertugliflozin relative to placebo was 0.97 with 95.6% confidence interval (0.85, 1.11). The upper bound of this confidence interval excluded a risk larger than 1.3 (Table 11). Results for the 5 mg and 15 mg doses were consistent with results for the combined dose group.

Table 11: Analysis of MACE and its Components from the VERTIS-CV Study [Intent-to-treat analysis set.]
Endpoint [MACE was evaluated in subjects who took at least one dose of study medication and, for subjects who discontinued study medication prior to the end of the study, censored events that occurred more than 365 days after the last dose of study medication. Other endpoints were evaluated using all randomized subjects and events that occurred any time after the first dose of study medication until the last contact date. The total number of first events was analyzed for each endpoint.] | Placebo (N=2747) |  | ertugliflozin (N=5499) |  | Hazard Ratio vs Placebo (CI) [HR and CI are based on Cox proportional hazards regression model, stratified by cohorts. For MACE a 95.6% CI is presented, for other endpoints a 95% CI is presented.]
Endpoint [MACE was evaluated in subjects who took at least one dose of study medication and, for subjects who discontinued study medication prior to the end of the study, censored events that occurred more than 365 days after the last dose of study medication. Other endpoints were evaluated using all randomized subjects and events that occurred any time after the first dose of study medication until the last contact date. The total number of first events was analyzed for each endpoint.] | N (%) | Event Rate (per 100 person-years) | N (%) | Event Rate (per 100 person-years) | Hazard Ratio vs Placebo (CI) [HR and CI are based on Cox proportional hazards regression model, stratified by cohorts. For MACE a 95.6% CI is presented, for other endpoints a 95% CI is presented.]
MACE (CV death, non-fatal MI, or non-fatal stroke) Composite | 327 (11.9) | 4.0 | 653 (11.9) | 3.9 | 0.97 (0.85, 1.11)
Components of Composite Endpoint
Non-fatal MI | 148 (5.4) | 1.6 | 310 (5.6) | 1.7 | 1.04 (0.86, 1.27)
Non-fatal Stroke | 78 (2.8) | 0.8 | 157 (2.9) | 0.8 | 1.00 (0.76, 1.32)
CV death | 184 (6.7) | 1.9 | 341 (6.2) | 1.8 | 0.92 (0.77, 1.11)
N=Number of patients, CI=Confidence interval, CV=Cardiovascular, MI=Myocardial infarction.

16 HOW SUPPLIED/STORAGE AND HANDLING

SEGLUROMET (ertugliflozin and metformin hydrochloride) tablets are available as follows:

Strength | Description | How Supplied | NDC
ertugliflozin 2.5 mg and metformin hydrochloride 500 mg tablets | pink, oval, debossed with “2.5/500” on one side and plain on the other side | unit-of-use bottles of 60 | 0006-5369-03
ertugliflozin 2.5 mg and metformin hydrochloride 500 mg tablets | pink, oval, debossed with “2.5/500” on one side and plain on the other side | unit-of-use bottles of 180 | 0006-5369-06
ertugliflozin 2.5 mg and metformin hydrochloride 1,000 mg tablets | pink, oval, debossed with “2.5/1000” on one side and plain on the other side | unit-of-use bottles of 60 | 0006-5373-03
ertugliflozin 2.5 mg and metformin hydrochloride 1,000 mg tablets | pink, oval, debossed with “2.5/1000” on one side and plain on the other side | unit-of-use bottles of 180 | 0006-5373-06
ertugliflozin 7.5 mg and metformin hydrochloride 500 mg tablets | red, oval, debossed with “7.5/500” on one side and plain on the other side | unit-of-use bottles of 60 | 0006-5370-03
ertugliflozin 7.5 mg and metformin hydrochloride 500 mg tablets | red, oval, debossed with “7.5/500” on one side and plain on the other side | unit-of-use bottles of 180 | 0006-5370-06
ertugliflozin 7.5 mg and metformin hydrochloride 1,000 mg tablets | red, oval, debossed with “7.5/1000” on one side and plain on the other side | unit-of-use bottles of 60 | 0006-5374-03
ertugliflozin 7.5 mg and metformin hydrochloride 1,000 mg tablets | red, oval, debossed with “7.5/1000” on one side and plain on the other side | unit-of-use bottles of 180 | 0006-5374-06

STORAGE AND HANDLING

Store at 20°C-25°C (68°F-77°F), excursions permitted between 15°C-30°C (between 59°F-86°F) [see USP Controlled Room Temperature]. Protect from moisture. Store in a dry place.

17 PATIENT COUNSELING INFORMATION

Advise the patient to read the FDA-approved patient labeling (Medication Guide).

Lactic Acidosis

Inform patients of the risks of lactic acidosis due to the metformin component, its symptoms, and conditions that predispose to its development [see Warnings and Precautions (5.1)]. Advise patients to discontinue SEGLUROMET immediately and to notify their doctor promptly if unexplained hyperventilation, malaise, myalgia, unusual somnolence, slow or irregular heartbeat, sensation of feeling cold (especially in the extremities), or other nonspecific symptoms occur. GI symptoms are common during initiation of metformin treatment and may occur during initiation of SEGLUROMET therapy; however, advise patients to consult their doctor if they develop unexplained symptoms. Although GI symptoms that occur after stabilization are unlikely to be drug related, such an occurrence of symptoms should be evaluated to determine if it may be due to metformin-induced lactic acidosis or other serious disease.

Diabetic Ketoacidosis in Patients with Type 1 Diabetes Mellitus and Other Ketoacidosis

Inform patients that SEGLUROMET can cause potentially fatal ketoacidosis and that type 2 diabetes mellitus and pancreatic disorders (e.g., history of pancreatitis or pancreatic surgery) are risk factors.

Educate all patients on precipitating factors (such as insulin dose reduction or missed insulin doses, infection, reduced caloric intake, ketogenic diet, surgery, dehydration, and alcohol abuse) and symptoms of ketoacidosis (including nausea, vomiting, abdominal pain, tiredness, and labored breathing). Inform patients that blood glucose may be normal even in the presence of ketoacidosis.

Advise patients that they may be asked to monitor ketones. If symptoms of ketoacidosis occur, instruct patients to discontinue SEGLUROMET and seek medical attention immediately [see Warnings and Precautions (5.2)].

Lower Limb Amputation

Inform patients of the potential for an increased risk of amputations. Counsel patients about the importance of routine preventative foot care. Instruct patients to monitor for new pain or tenderness, sores or ulcers, or infections involving the leg or foot and to seek medical advice immediately if such signs or symptoms develop [see Warnings and Precautions (5.3)].

Volume Depletion

Inform patients that symptomatic hypotension may occur with SEGLUROMET and advise them to contact their doctor if they experience such symptoms [see Warnings and Precautions (5.4)]. Inform patients that dehydration may increase the risk for hypotension, and to have adequate fluid intake.

Serious Urinary Tract Infections

Inform patients of the potential for urinary tract infections, which may be serious. Provide them with information on the symptoms of urinary tract infections. Advise them to seek medical advice if such symptoms occur [see Warnings and Precautions (5.5)].

Hypoglycemia with Concomitant Use of Insulin or Insulin Secretagogue

Inform patients that the incidence of hypoglycemia may increase when SEGLUROMET is used with insulin or an insulin secretagogue. Educate patients or caregivers on the signs and symptoms of hypoglycemia [see Warnings and Precautions (5.6)].

Necrotizing Fasciitis of the Perineum (Fournier's Gangrene)

Inform patients that necrotizing infections of the perineum (Fournier's Gangrene) have occurred with SGLT2 inhibitors. Counsel patients to promptly seek medical attention if they develop pain or tenderness, redness, or swelling of the genitals or the area from the genitals back to the rectum, along with a fever above 100.4°F or malaise [see Warnings and Precautions (5.7)].

Genital Mycotic Infections in Females (e.g., Vulvovaginitis)

Inform female patients that vaginal yeast infections may occur and provide them with information on the signs and symptoms of vaginal yeast infection. Advise them of treatment options and when to seek medical advice [see Warnings and Precautions (5.8)].

Genital Mycotic Infections in Males (e.g., Balanitis or Balanoposthitis)

Inform male patients that yeast infections of the penis (e.g., balanitis or balanoposthitis) may occur, especially in uncircumcised males. Provide them with information on the signs and symptoms of balanitis and balanoposthitis (rash or redness of the glans or foreskin of the penis). Advise them of treatment options and when to seek medical advice [see Warnings and Precautions (5.8)].

Fetal Toxicity

Advise pregnant patients of the potential risk to a fetus with treatment with SEGLUROMET. Instruct patients to immediately inform their healthcare provider if pregnant or planning to become pregnant [see Use in Specific Populations (8.1)].

Lactation

Advise patients that use of SEGLUROMET is not recommended while breastfeeding [see Use in Specific Populations (8.2)].

Pregnancy

Inform female patients that treatment with metformin may result in an unintended pregnancy in some premenopausal anovulatory females due to its effect on ovulation [see Use in Specific Populations (8.3)].

Laboratory Tests

Due to the mechanism of action of ertugliflozin, inform patients that their urine will test positive for glucose while taking SEGLUROMET.

Missed Dose

Instruct patients to take SEGLUROMET only as prescribed. If a dose is missed, it should be taken as soon as the patient remembers. Advise patients not to double their next dose.

Manufactured for: Merck Sharp & Dohme LLC
Rahway, NJ 07065, USA

For patent information: www.msd.com/research/patent

Copyright © 2017-2024 Merck & Co., Inc., Rahway, NJ, USA, and its affiliates.
All rights reserved.

uspi-mk8835b-t-2412r010

Medication Guide
SEGLUROMET® [seg-LUR-oh-met]
(ertugliflozin and metformin hydrochloride)
tablets, for oral use

Read this Medication Guide carefully before you start taking SEGLUROMET and each time you get a refill. There may be new information. This information does not take the place of talking with your healthcare provider about your medical condition or your treatment.

What is the most important information I should know about SEGLUROMET?
SEGLUROMET may cause serious side effects, including:
Lactic Acidosis. Metformin, one of the medicines in SEGLUROMET, can cause a rare but serious condition called lactic acidosis (a buildup of an acid in the blood) that can cause death. Lactic acidosis is a medical emergency and must be treated in the hospital.
Call your healthcare provider right away if you have any of the following symptoms, which could be signs of lactic acidosis:

- you feel cold in your hands or feet
- you feel very weak or tired
- you have trouble breathing
- you have stomach pains, nausea or vomiting

- you have a slow or irregular heartbeat
- you have unusual (not normal) muscle pain
- you have unusual sleepiness or sleep longer than usual
- you feel dizzy or lightheaded

Most people who have had lactic acidosis had other conditions that, in combination with metformin use, led to the lactic acidosis. Tell your healthcare provider if you have any of the following, because you have a higher chance for getting lactic acidosis with SEGLUROMET if you:

- have severe kidney problems or your kidneys are affected by certain x-ray tests that use injectable dye.
- have liver problems.
- drink alcohol very often or drink a lot of alcohol in the short term ("binge") drinking.
- get dehydrated (lose a large amount of body fluids). This can happen if you are sick with a fever, vomiting, or diarrhea. Dehydration can also happen when you sweat a lot with activity or exercise and do not drink enough fluids.
- have surgery.
- have a heart attack, severe infection, or stroke.

The best way to keep from having a problem with lactic acidosis from metformin is to tell your healthcare provider if you have any of the problems in the list above. Your healthcare provider may decide to stop your SEGLUROMET for a while if you have any of these things.

- Diabetic ketoacidosis (increased ketones in your blood or urine) in people with type 1 diabetes and other ketoacidosis. SEGLUROMET can cause ketoacidosis that can be life-threatening and may lead to death. Ketoacidosis is a serious condition which needs to be treated in a hospital. People with type 1 diabetes have a high risk of getting ketoacidosis. People with type 2 diabetes or pancreas problems also have an increased risk of getting ketoacidosis. Ketoacidosis can also happen in people who are sick, cannot eat or drink as usual, skip meals, are on a diet high in fat and low in carbohydrates (ketogenic diet), take less than the usual amount of insulin or miss insulin doses, drink too much alcohol, have a loss of too much fluid from the body (volume depletion), or who have surgery. Ketoacidosis can happen even if your blood sugar is less than 250 mg/dL. Your healthcare provider may ask you to periodically check ketones in your urine or blood.
  Stop taking SEGLUROMET and call your healthcare provider or get medical help right away if you get any of the following. If possible, check for ketones in your urine or blood, even if your blood sugar is less than 250 mg/dL:

- nausea
- vomiting
- stomach-area (abdominal) pain

- tiredness
- trouble breathing
- ketones in your urine or blood

SEGLUROMET can have other serious side effects. See "What are the possible side effects of SEGLUROMET?"

What is SEGLUROMET?

- SEGLUROMET contains 2 prescription medicines called ertugliflozin (STEGLATRO®) and metformin hydrochloride. SEGLUROMET is used in adults with type 2 diabetes to improve blood sugar (glucose) along with diet and exercise.
- SEGLUROMET is not recommended to decrease blood sugar (glucose) in people with type 1 diabetes. It is not known if SEGLUROMET is safe and effective in children under 18 years of age.

Who should not take SEGLUROMET?
Do not take SEGLUROMET if you:

- have severe kidney problems, have end stage renal disease (ESRD) or are on dialysis.
- have a condition called metabolic acidosis or diabetic ketoacidosis (increased ketones in the blood or urine).
- are allergic to ertugliflozin, metformin, or any of the ingredients in SEGLUROMET. See the end of this Medication Guide for a list of ingredients in SEGLUROMET. Symptoms of a serious allergic reaction to SEGLUROMET may include:
  - skin rash
  - raised red patches on your skin (hives)
  - swelling of the face, lips, tongue, and throat that may cause difficulty in breathing or swallowing

If you have any of these symptoms, stop taking SEGLUROMET and call your healthcare provider right away or go to the nearest hospital emergency room.

Before you take SEGLUROMET, tell your healthcare provider about all of your medical conditions, including if you:

- have type 1 diabetes or have had diabetic ketoacidosis.
- have a decrease in your insulin dose.
- have a serious infection.
- have a history of infection of the vagina or penis.
- have a history of amputation.
- have had blocked or narrowed blood vessels, usually in the leg.
- have damage to the nerves (neuropathy) in your leg.
- have had diabetic foot ulcers or sores.
- have kidney problems.
- have liver problems.
- have a history of urinary tract infections or problems with urination.
- are on a low sodium (salt) diet. Your healthcare provider may change your diet or your dose.
- have heart problems, including congestive heart failure.
- are going to have surgery. Your healthcare provider may stop your SEGLUROMET before you have surgery. Talk to your healthcare provider if you are having surgery about when to stop taking SEGLUROMET and when to start it again.
- are eating less or there is a change in your diet.
- are dehydrated.
- have or have had problems with your pancreas, including pancreatitis or surgery on your pancreas.
- drink alcohol very often or drink a lot of alcohol in the short term (“binge” drinking).
- have ever had an allergic reaction to SEGLUROMET.
- are going to get an injection of dye or contrast agents for an x-ray procedure. SEGLUROMET may need to be stopped for a short time. Talk to your healthcare provider about when you should stop SEGLUROMET and when you should start SEGLUROMET again. See "What is the most important information I should know about SEGLUROMET?"
- are pregnant or plan to become pregnant. SEGLUROMET may harm your unborn baby. If you become pregnant while taking SEGLUROMET, your healthcare provider may switch you to a different medicine to control your blood sugar. Talk to your healthcare provider about the best way to control your blood sugar if you plan to become pregnant or while you are pregnant.
- are a premenopausal woman (before the “change of life”), who does not have periods regularly or at all. Talk to your healthcare provider about birth control choices while taking SEGLUROMET if you are not planning to become pregnant since SEGLUROMET may increase your chance of becoming pregnant. Tell your healthcare provider right away if you become pregnant while taking SEGLUROMET.
- are breastfeeding or plan to breastfeed. It is not known if SEGLUROMET passes into your breast milk. You should not breastfeed if you take SEGLUROMET.

Tell your healthcare provider about all of the medicines you take, including prescription and over-the-counter medicines, vitamins, and herbal supplements.
SEGLUROMET may affect the way other medicines work, and other medicines may affect how SEGLUROMET works.
Know the medicines you take. Keep a list of them to show your healthcare provider and pharmacist when you get a new medicine.

How should I take SEGLUROMET?

- Take SEGLUROMET by mouth 2 times a day with meals, exactly as your healthcare provider tells you to take it. Taking SEGLUROMET with meals may lower your chance of having an upset stomach.
- Your healthcare provider may tell you to take SEGLUROMET along with other diabetes medicines. Low blood sugar can happen more often when SEGLUROMET is taken with certain other diabetes medicines. See "What are the possible side effects of SEGLUROMET?"
- If you miss a dose, take it as soon as you remember. If it is almost time for your next dose, skip the missed dose and take the medicine at the next regularly scheduled time. Do not take 2 doses of SEGLUROMET at the same time. Talk with your healthcare provider if you have questions about a missed dose.
- If you take too much SEGLUROMET, call your healthcare provider or go to the nearest hospital emergency room right away.
- When your body is under some types of stress, such as fever, trauma (such as a car accident), infection, or surgery, the amount of diabetes medicine you need may change. Tell your healthcare provider right away if you have any of these conditions and follow your healthcare provider’s instructions.
- SEGLUROMET will cause your urine to test positive for glucose.
- Your healthcare provider may do certain blood tests before you start SEGLUROMET and during treatment as needed. Your healthcare provider may change your dose of SEGLUROMET based on the results of your blood tests.

What should I avoid while taking SEGLUROMET?

- Avoid drinking alcohol very often or drinking a lot of alcohol in a short period of time ("binge" drinking). It can increase your chances of getting serious side effects.

What are the possible side effects of SEGLUROMET?
SEGLUROMET may cause serious side effects, including:
See "What is the most important information I should know about SEGLUROMET?"

- Amputations. SEGLUROMET may increase your risk of lower limb amputations.
  You may be at a higher risk of lower limb amputation if you:
  - have a history of amputation
  - have had blocked or narrowed blood vessels, usually in your leg
  - have damage to the nerves (neuropathy) in your leg
  - have had diabetic foot ulcers or sores

Call your healthcare provider right away if you have new pain or tenderness, any sores, ulcers, or infections in your leg or foot. Your healthcare provider may decide to stop your SEGLUROMET for a while if you have any of these signs or symptoms. Talk to your healthcare provider about proper foot care.

- Dehydration. SEGLUROMET can cause some people to become dehydrated (the loss of body water and salt). Dehydration may cause you to feel dizzy, faint, lightheaded, or weak, especially when you stand up (orthostatic hypotension). There have been reports of sudden worsening of kidney function in people who are taking SEGLUROMET.
  You may be at risk of dehydration if you:
  - take medicines to lower your blood pressure, including water pills (diuretics)
  - are on a low sodium (salt) diet
  - have kidney problems
  - are 65 years of age or older

Talk to your healthcare provider about what you can do to prevent dehydration including how much fluid you should drink on a daily basis. Call your healthcare provider right away if you reduce the amount of food or liquid you drink, for example if you are sick or cannot eat, or you start to lose liquids from your body, for example from vomiting, diarrhea or being in the sun too long.

- Serious urinary tract infections. Serious urinary tract infections that may lead to hospitalization have happened in people who are taking SEGLUROMET. Tell your healthcare provider if you have any signs or symptoms of a urinary tract infection such as a burning feeling when passing urine, a need to urinate often, the need to urinate right away, pain in the lower part of your stomach (pelvis), or blood in the urine. Sometimes people may also have a fever, back pain, nausea, or vomiting.

- Low blood sugar (hypoglycemia). If you take SEGLUROMET with another medicine that can cause low blood sugar such as a sulfonylurea or insulin, your risk of getting low blood sugar is higher. The dose of your sulfonylurea or insulin may need to be lowered while you take SEGLUROMET. Signs and symptoms of low blood sugar may include:

- headache
- confusion
- hunger
- shaking or feeling jittery

- drowsiness
- dizziness
- fast heartbeat

- weakness
- sweating
- irritability

- A rare but serious bacterial infection that causes damage to the tissue under the skin (necrotizing fasciitis) in the area between and around the anus and genitals (perineum). Necrotizing fasciitis of the perineum has happened in women and men who take medicines that lower blood sugar in the same way as one of the medicines in SEGLUROMET. Necrotizing fasciitis of the perineum may lead to hospitalization, may require multiple surgeries, and may lead to death. Seek medical attention immediately if you have fever above 100.4°F or you are feeling very weak, tired or uncomfortable (malaise) and you develop any of the following symptoms in the area between and around your anus and genitals:

- pain or tenderness

- swelling

- redness of skin (erythema)

- Vaginal yeast infection. Symptoms of a vaginal yeast infection include:
  - vaginal odor
  - white or yellowish vaginal discharge (discharge may be lumpy or look like cottage cheese)
  - vaginal itching
- Yeast infection of the penis (balanitis or balanoposthitis). Swelling of an uncircumcised penis may develop that makes it difficult to pull back the skin around the tip of the penis. Other symptoms of yeast infection of the penis include:

- redness, itching, or swelling of the penis
- foul smelling discharge from the penis

- rash of the penis
- pain in the skin around your penis

Talk to your healthcare provider about what to do if you get symptoms of a yeast infection of the vagina or penis. Your healthcare provider may suggest you use an over-the-counter antifungal medicine. Talk to your healthcare provider right away if you use an over-the-counter antifungal medicine and your symptoms do not go away.

- Low vitamin B12 (vitamin B12 deficiency). Using metformin for long periods of time may cause a decrease in the amount of vitamin B12 in your blood, especially if you have had low vitamin B12 blood levels before. Your healthcare provider may do blood tests to check your vitamin B12 levels.
- Serious allergic reaction. If you have any symptoms of a serious allergic reaction, stop taking SEGLUROMET and call your healthcare provider right away or go to the nearest hospital emergency room. See “Who should not take SEGLUROMET?”. Your healthcare provider may give you a medicine for your allergic reaction and prescribe a different medicine for your diabetes

The most common side effects of ertugliflozin include:

- vaginal yeast infections and yeast infections of the penis (See "What is the most important information I should know about SEGLUROMET?")
- changes in urination, including urgent need to urinate more often, in larger amounts, or at night

The most common side effects of metformin hydrochloride include:

- diarrhea
- nausea
- stomach discomfort

- vomiting
- gas
- headache

- indigestion
- weakness

These are not all the possible side effects of SEGLUROMET.
Call your healthcare provider for medical advice about side effects. You may report side effects to FDA at 1-800-FDA-1088.

How should I store SEGLUROMET?

- Store SEGLUROMET at room temperature between 68°F to 77°F (20°C to 25°C).
- Keep SEGLUROMET dry.

Keep SEGLUROMET and all medicines out of the reach of children.

General information about the safe and effective use of SEGLUROMET.
Medicines are sometimes prescribed for purposes other than those listed in a Medication Guide. Do not use SEGLUROMET for a condition for which it was not prescribed. Do not give SEGLUROMET to other people, even if they have the same symptoms that you have. It may harm them. You can ask your pharmacist or healthcare provider for information about SEGLUROMET that is written for health professionals.
For more information about SEGLUROMET, go to www.segluromet.com or call 1-800-622-4477.

What are the ingredients in SEGLUROMET?
Active ingredients: ertugliflozin and metformin hydrochloride.
Inactive ingredients: povidone, microcrystalline cellulose, crospovidone, sodium lauryl sulfate, and magnesium stearate.
The tablet film coating contains the following inactive ingredients: hydroxypropyl methylcellulose, hydroxypropyl cellulose, titanium dioxide, iron oxide red, and carnauba wax.

Manufactured for: Merck Sharp & Dohme LLC
Rahway, NJ 07065, USA
For patent information, go to: www.msd.com/research/patent
Copyright © 2017-2023 Merck & Co., Inc., Rahway, NJ, USA, and its affiliates. All rights reserved.
usmg-mk8835b-t-2309r007

This Medication Guide has been approved by the U.S. Food and Drug Administration.

Revised: 09/2023

PRINCIPAL DISPLAY PANEL - 2.5 mg/500 mg Tablet Bottle Label

NDC 0006-5369-03

Segluromet®

(ertugliflozin and
metformin HCl) tablets

2.5 mg / 500 mg

Dispense the accompanying Medication Guide
to each patient.

Each tablet contains 3.24 mg ertugliflozin L-pyroglutamic
acid (equivalent to 2.5 mg ertugliflozin) and
500 mg of metformin hydrochloride.

Rx only

60 Tablets

PRINCIPAL DISPLAY PANEL - 2.5 mg/1,000 mg Tablet Bottle Label

NDC 0006-5373-03

Segluromet®
(ertugliflozin and
metformin HCl) tablets

2.5 mg / 1,000 mg

Dispense the accompanying Medication Guide
to each patient.

Each tablet contains 3.24 mg ertugliflozin
L-pyroglutamic acid (equivalent
to 2.5 mg ertugliflozin) and
1,000 mg of metformin
hydrochloride.

60 Tablets
Rx only

PRINCIPAL DISPLAY PANEL - 7.5 mg/500 mg Tablet Bottle Label

NDC 0006-5370-03

Segluromet®

(ertugliflozin and
metformin HCl) tablets

7.5 mg / 500 mg

Dispense the accompanying Medication Guide
to each patient.

Each tablet contains 9.71 mg ertugliflozin L-pyroglutamic
acid (equivalent to 7.5 mg ertugliflozin)
and 500 mg of metformin
hydrochloride.

Rx only

60 Tablets

PRINCIPAL DISPLAY PANEL - 7.5 mg/1,000 mg Tablet Bottle Label

NDC 0006-5374-03

Segluromet®
(ertugliflozin and
metformin HCl) tablets

7.5 mg / 1,000 mg

Dispense the accompanying Medication Guide
to each patient.

Each tablet contains 9.71 mg ertugliflozin L-pyroglutamic
acid (equivalent to 7.5 mg
ertugliflozin) and 1,000 mg
of metformin hydrochloride.

Rx only

60 Tablets